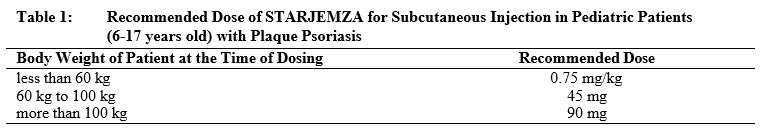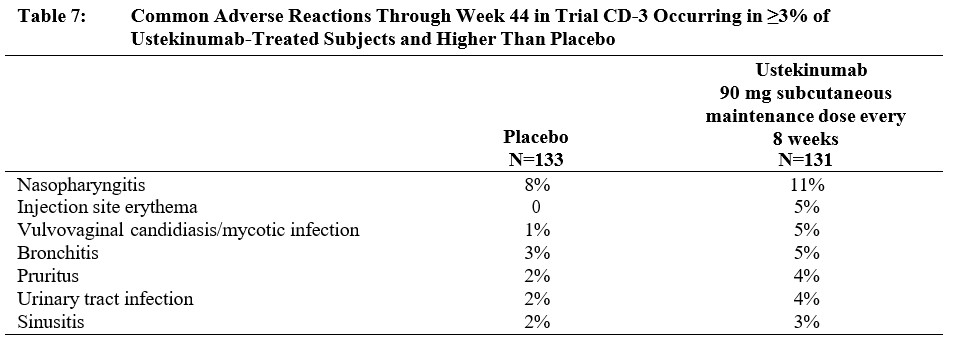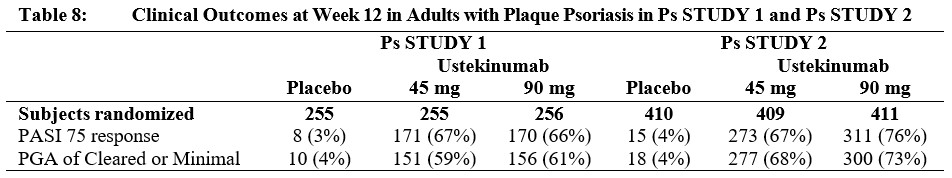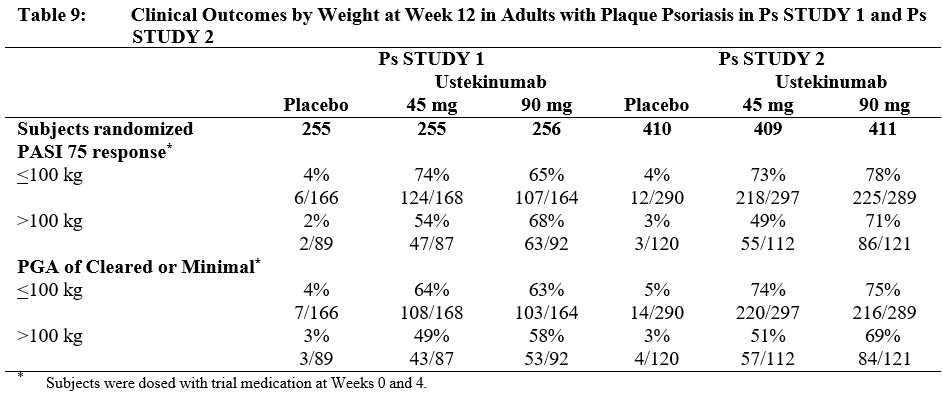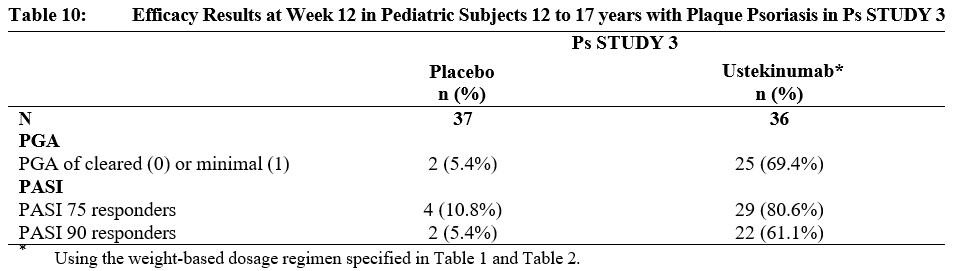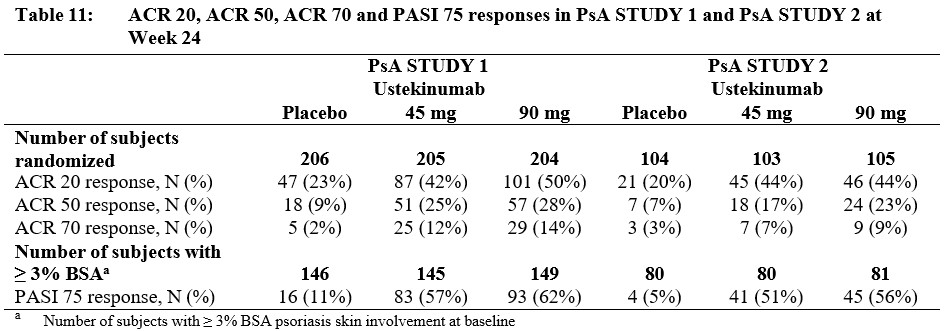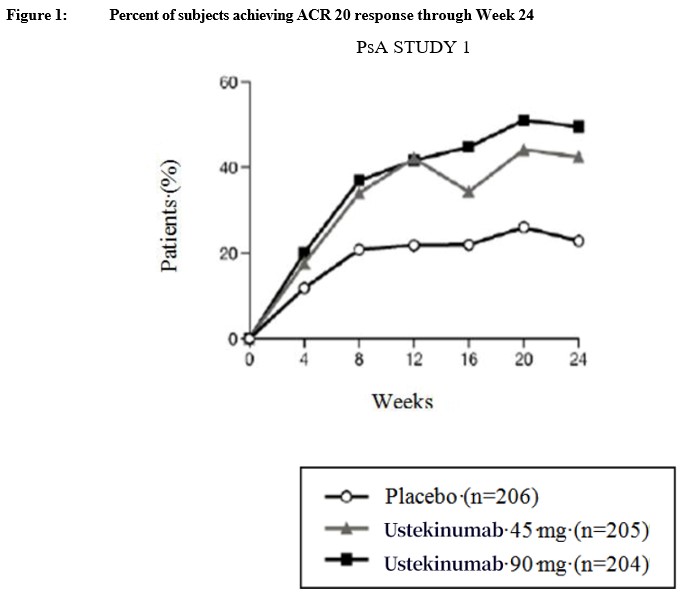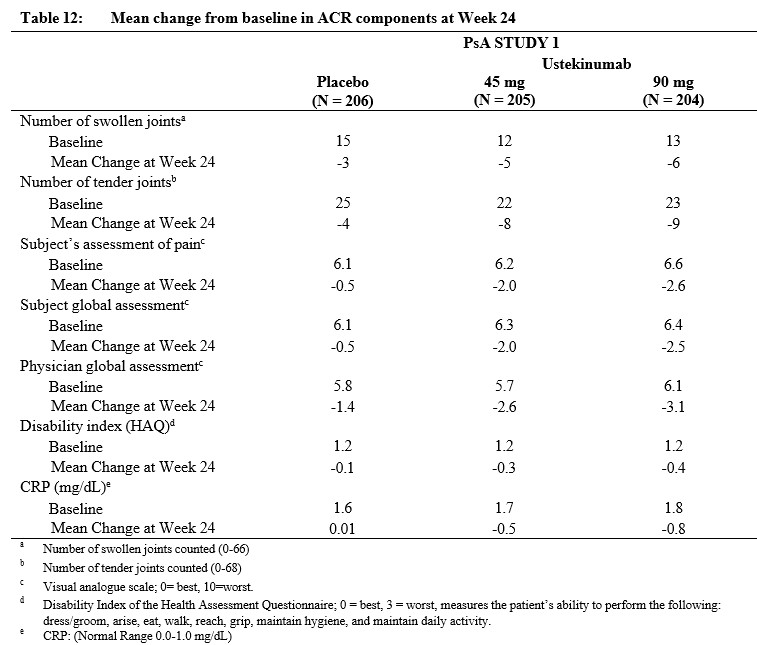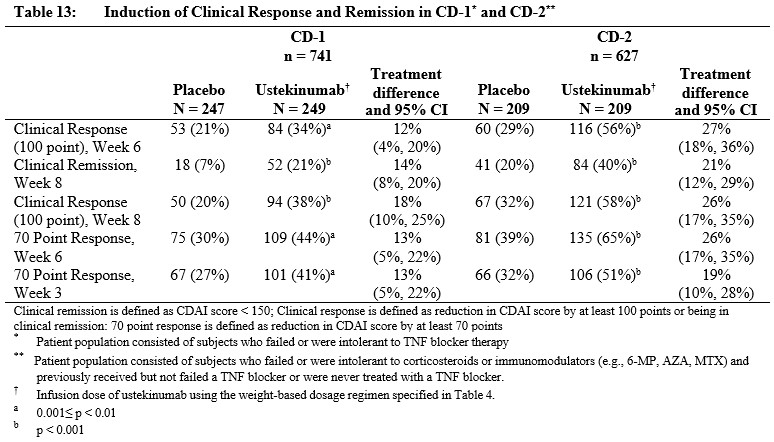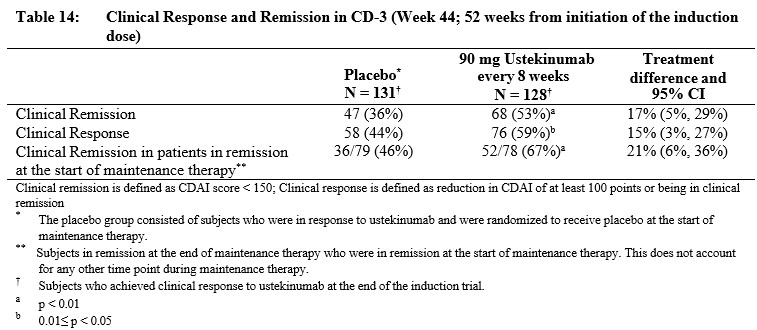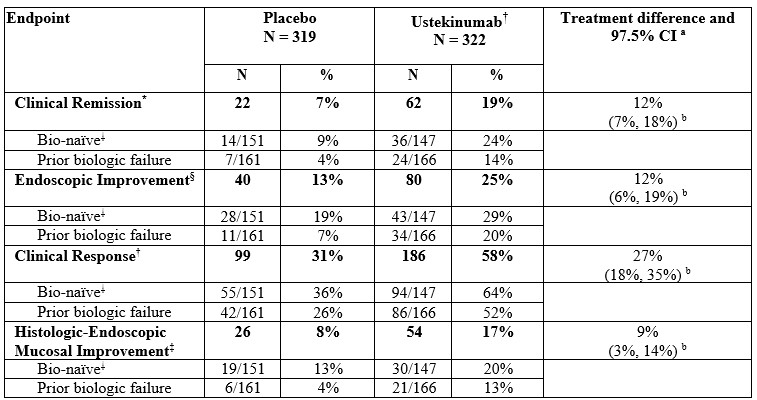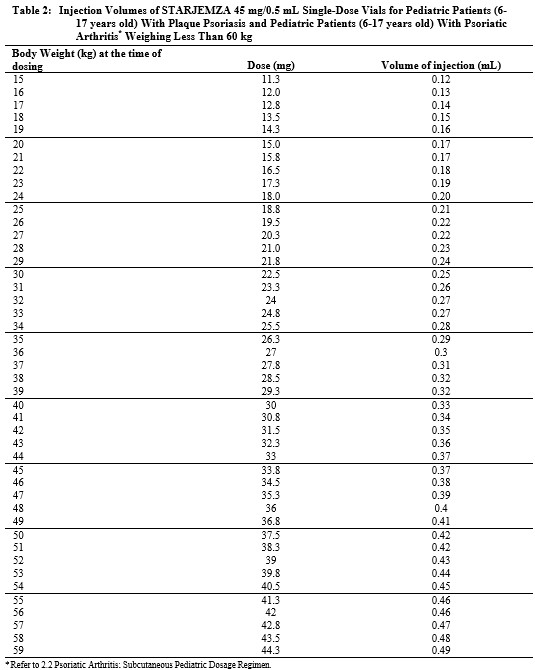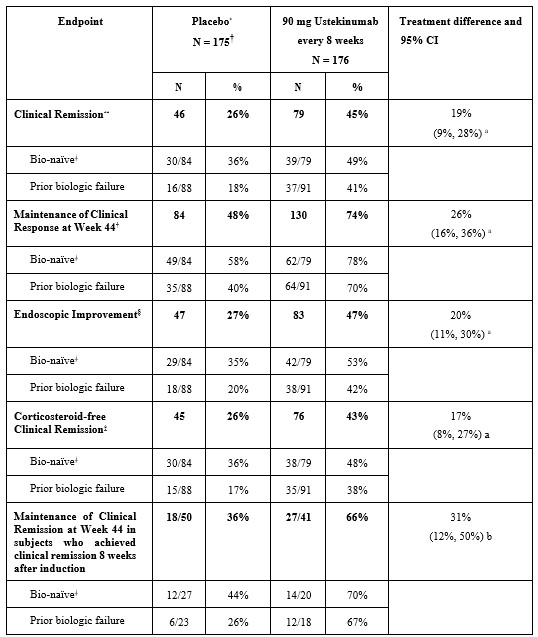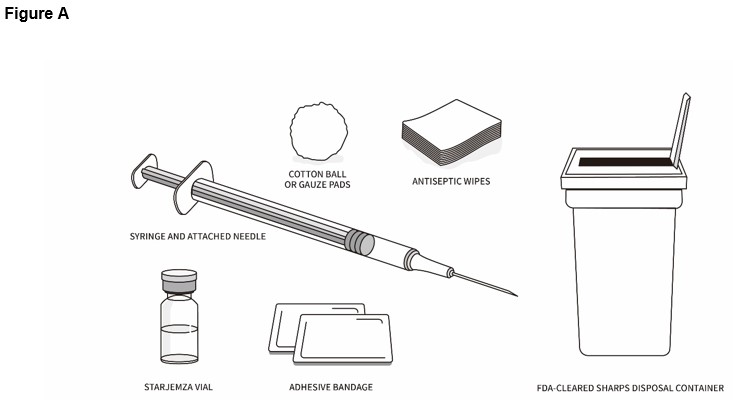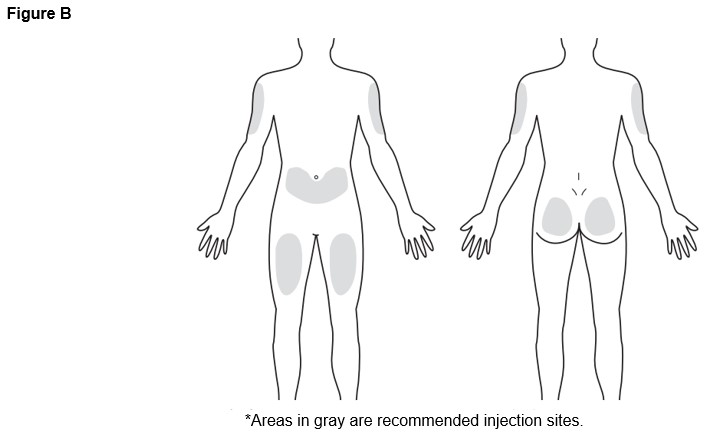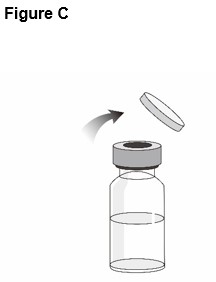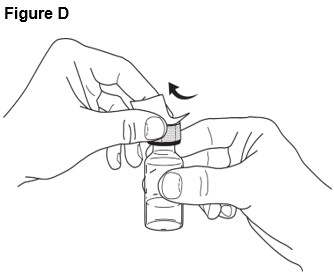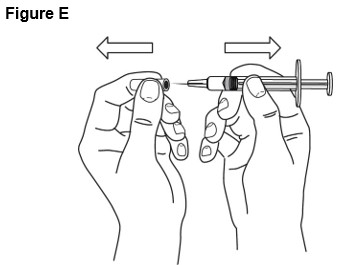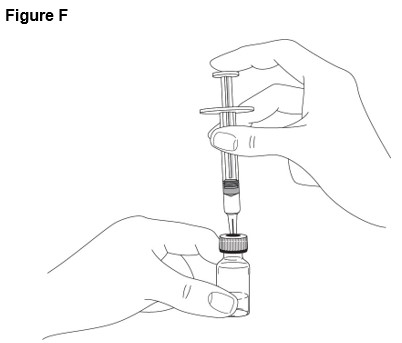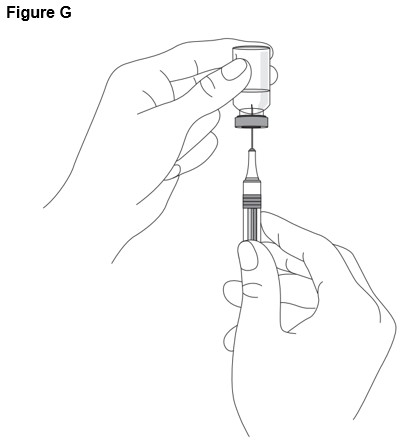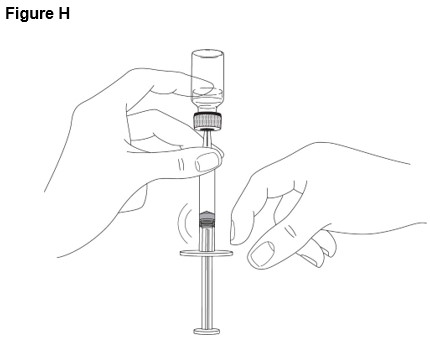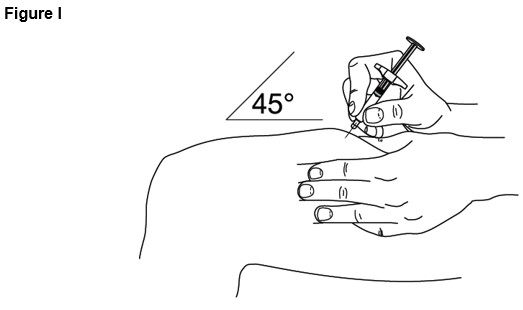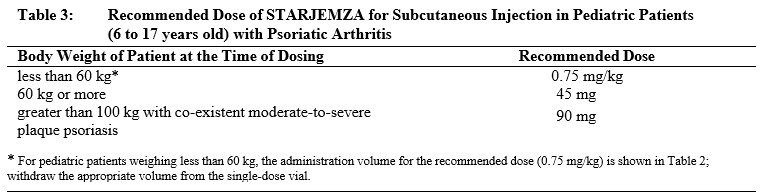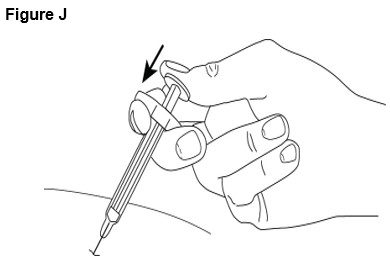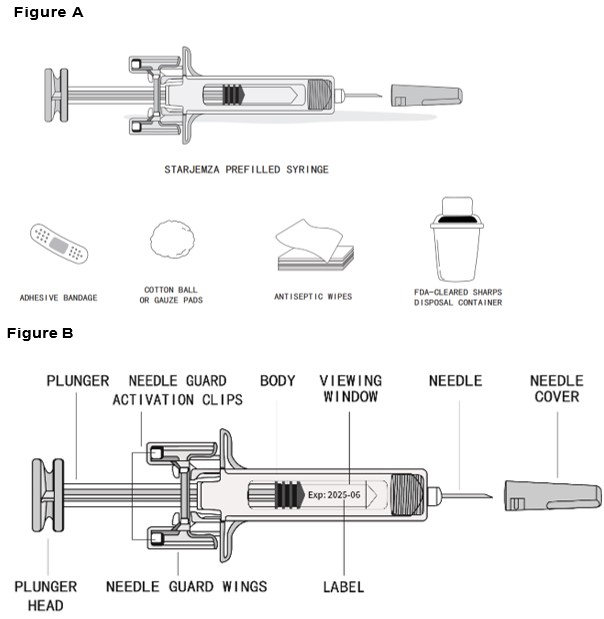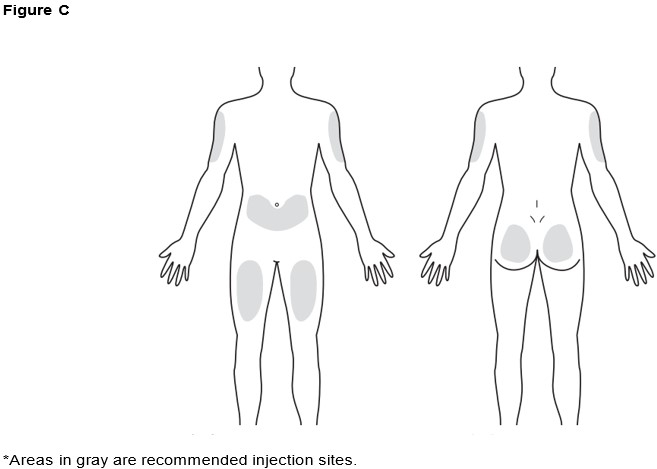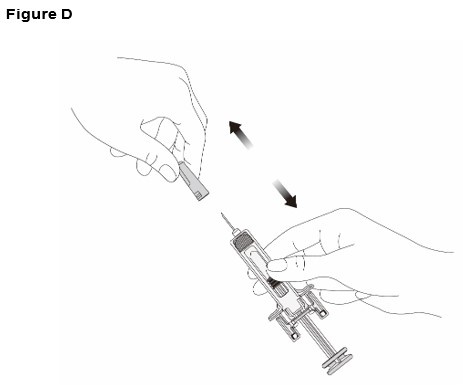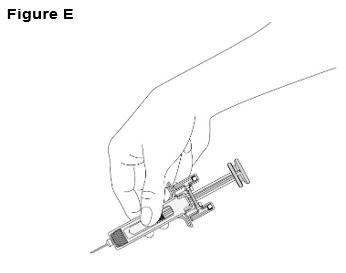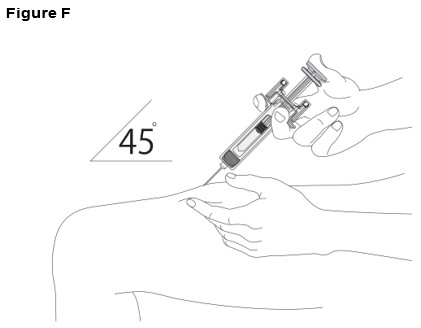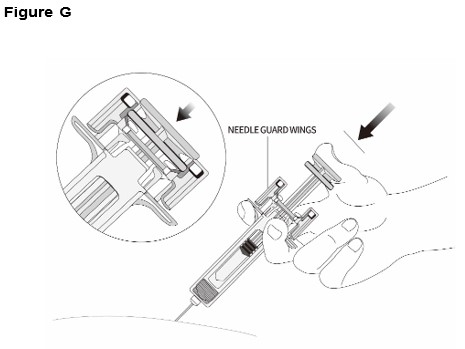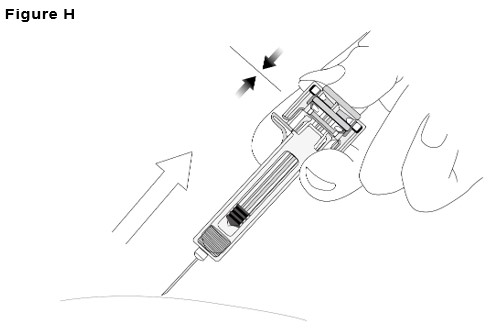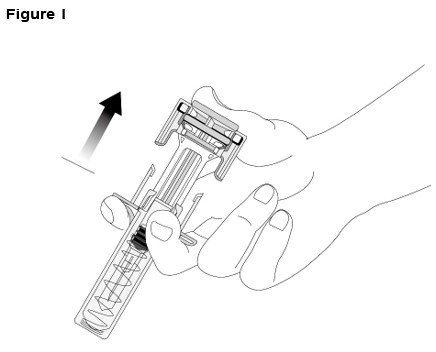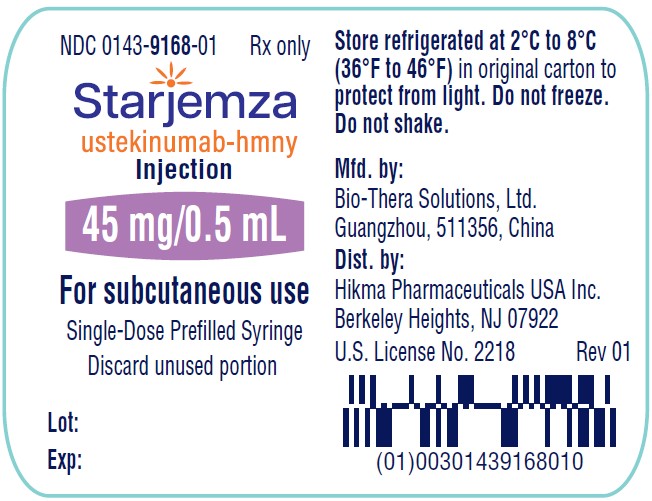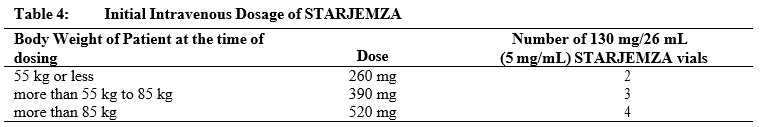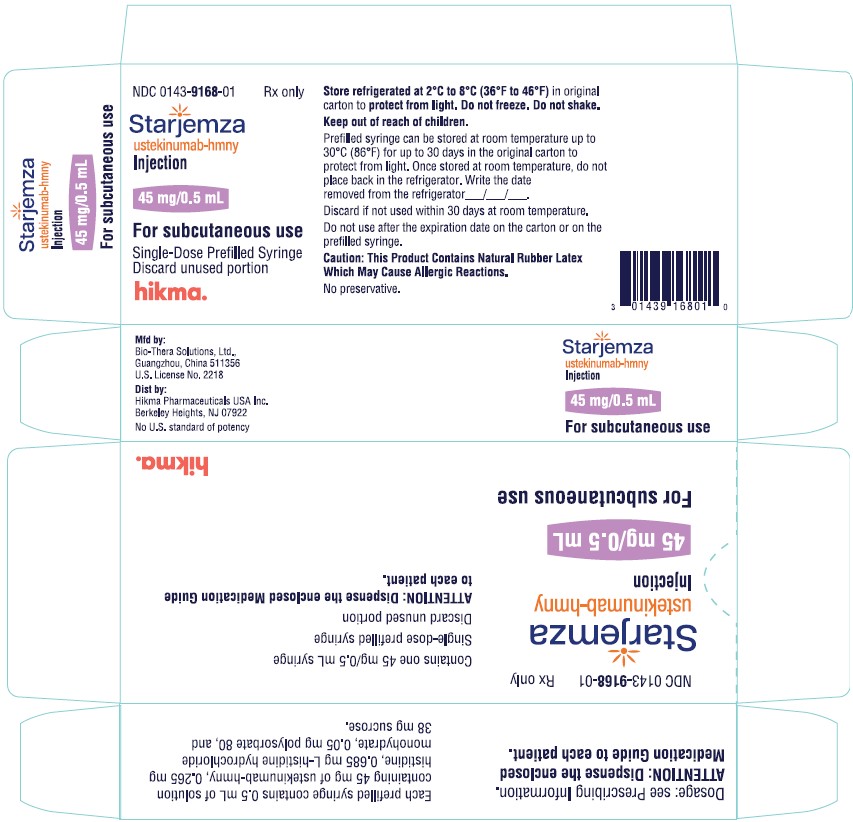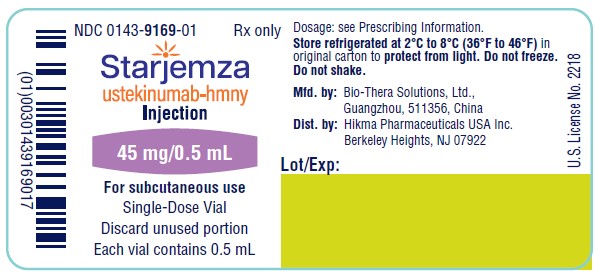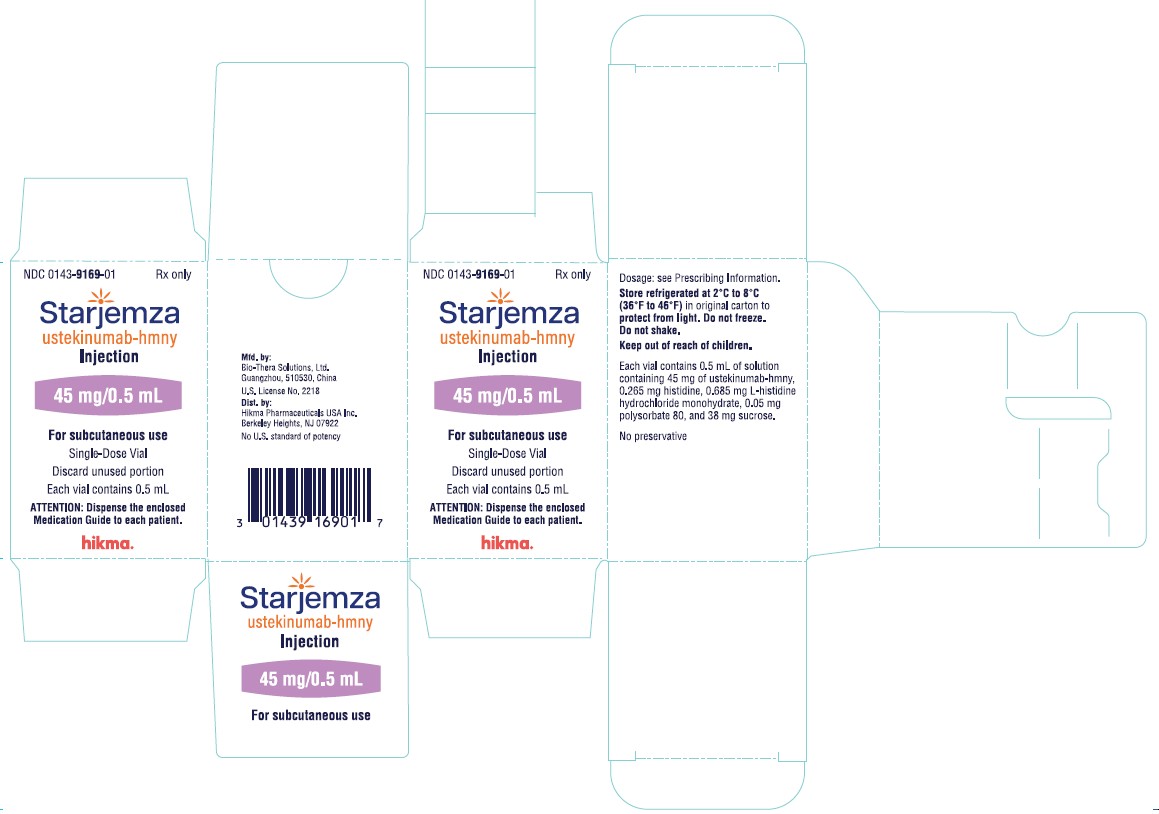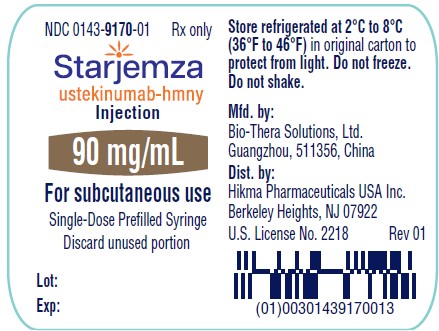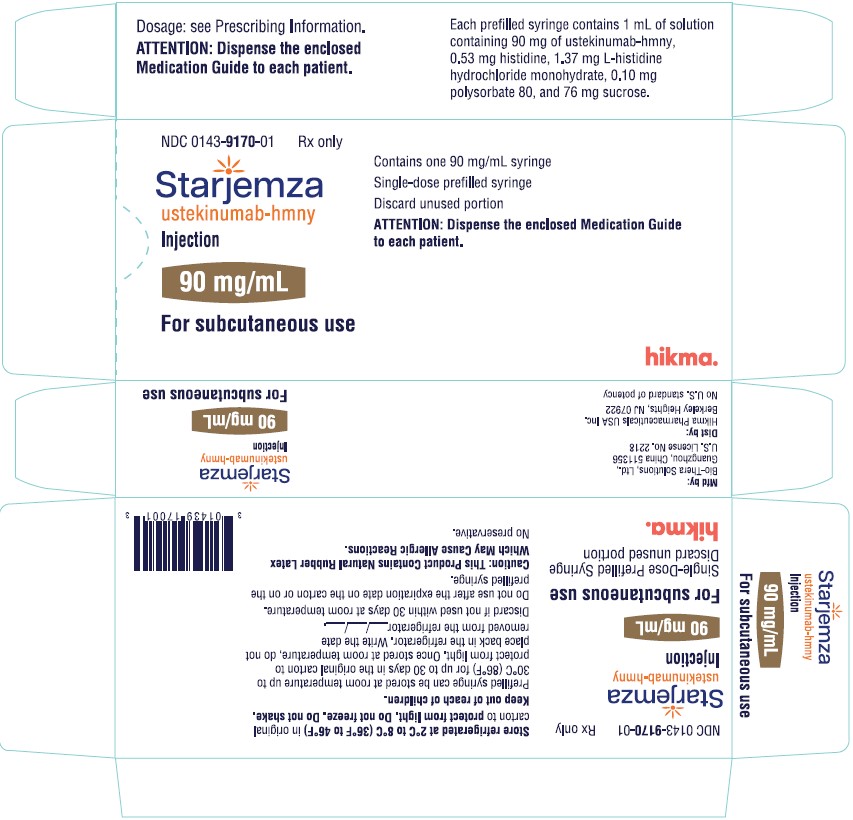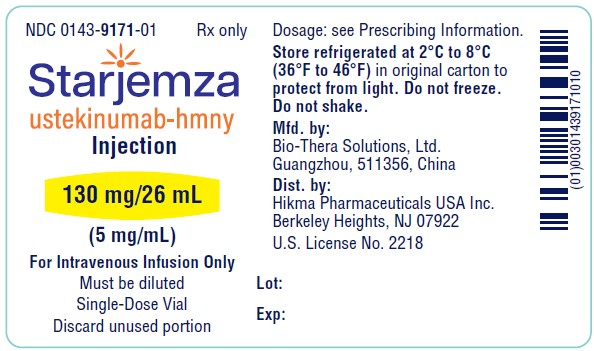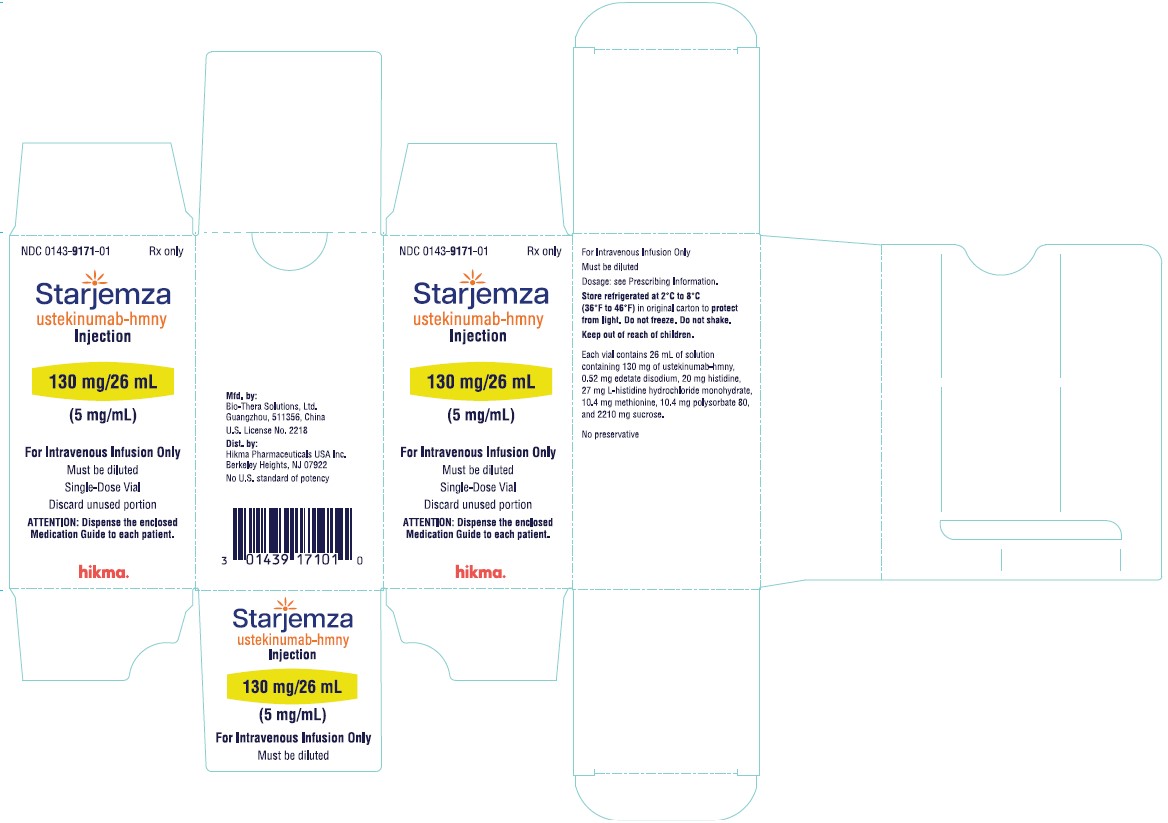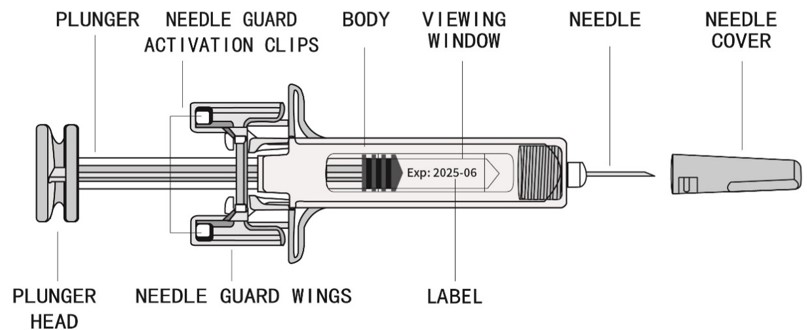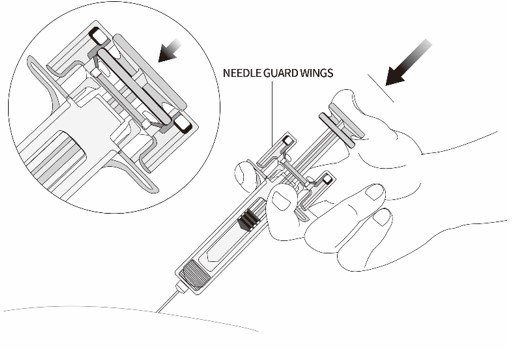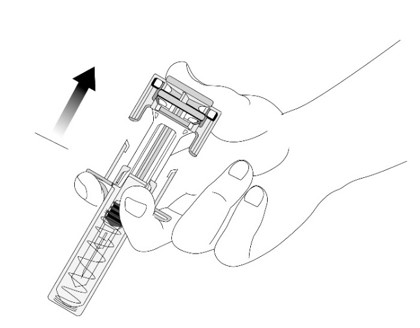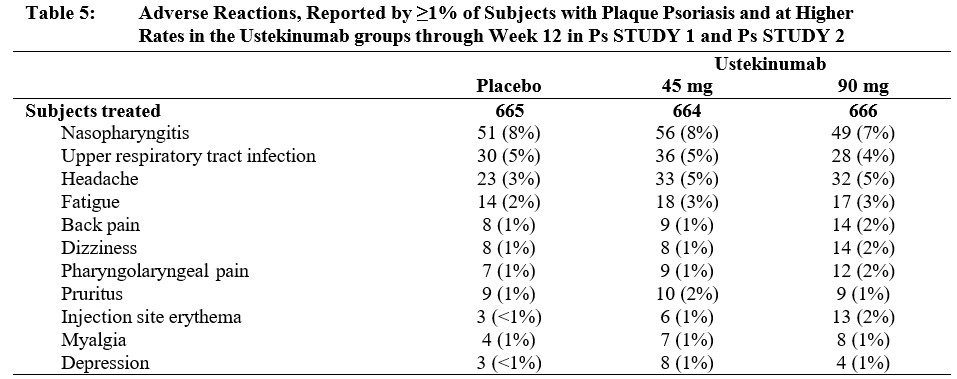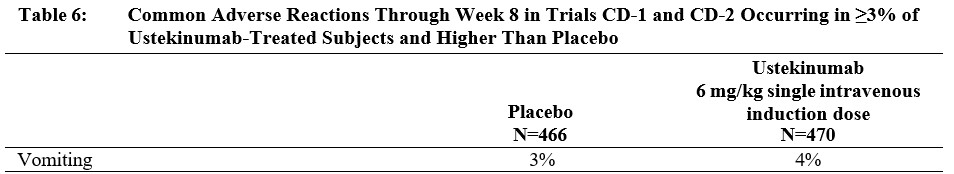 DRUG LABEL: Starjemza
NDC: 0143-9168 | Form: INJECTION
Manufacturer: Hikma Pharmaceuticals USA Inc.
Category: prescription | Type: HUMAN PRESCRIPTION DRUG LABEL
Date: 20251024

ACTIVE INGREDIENTS: USTEKINUMAB 45 mg/0.5 mL
INACTIVE INGREDIENTS: HISTIDINE 0.265 mg/0.5 mL; HISTIDINE HYDROCHLORIDE MONOHYDRATE 0.685 mg/0.5 mL; POLYSORBATE 80 0.05 mg/0.5 mL; SUCROSE 38 mg/0.5 mL

HIGHLIGHTS OF PRESCRIBING INFORMATION

These highlights do not include all the information needed to use STARJEMZA™ safely and effectively. See full prescribing information for STARJEMZA™.
STARJEMZA™ (ustekinumab-hmny) injection, for subcutaneous or intravenous use
Initial U.S. Approval: 2025
STARJEMZA™ (ustekinumab-hmny) is biosimilar* to STELARA® (ustekinumab).

1 INDICATIONS AND USAGE

STARJEMZA is a human interleukin-12 and -23 antagonist indicated for the treatment of:

Adult patients with:

- moderate to severe plaque psoriasis (PsO) who are candidates for phototherapy or systemic therapy. (1.1)
- active psoriatic arthritis (PsA). (1.2)
- moderately to severely active Crohn’s disease (CD). (1.3)
- moderately to severely active ulcerative colitis. (1.4)

Pediatric patients 6 years and older with:

- moderate to severe plaque psoriasis, who are candidates for phototherapy or systemic therapy. (1.1)
- active psoriatic arthritis (PsA). (1.2)

2 DOSAGE AND ADMINISTRATION

Psoriasis Adult Subcutaneous Recommended Dosage (2.1):

Weight Range (kilograms) | Recommended Dosage
less than or equal to 100 kg | 45 mg administered subcutaneously initially and 4 weeks later, followed by; 45 mg administered subcutaneously every 12 weeks
greater than 100 kg | 90 mg administered subcutaneously initially and 4 weeks later, followed by 90 mg administered subcutaneously; every 12 weeks

Psoriasis Pediatric Patients (6 to 17 years old) Subcutaneous Recommended Dosage (2.1): Weight-based dosing is recommended at the initial dose, 4 weeks later, then every 12 weeks thereafter.

Weight Range (kilograms) | Dose
less than 60 kg | 0.75 mg/kg
60 kg to 100 kg | 45 mg
greater than 100 kg | 90 mg

Psoriatic Arthritis Adult Subcutaneous Recommended Dosage (2.2):

- The recommended dosage is 45 mg administered subcutaneously initially and 4 weeks later, followed by 45 mg administered subcutaneously every 12 weeks.
- For patients with co-existent moderate-to-severe plaque psoriasis weighing greater than 100 kg, the recommended dosage is 90 mg administered subcutaneously initially and 4 weeks later, followed by 90 mg administered subcutaneously every 12 weeks.

Psoriatic Arthritis Pediatric (6 to 17 years old) Subcutaneous Recommended Dosage (2.2): Weight-based dosing is recommended at the initial dose, 4 weeks later, then every 12 weeks thereafter.

Weight Range (kilograms) | Dose
less than 60 kg | 0.75 mg/kg
60 kg or more | 45 mg
greater than 100 kg with co- existent moderate-to-severe plaque psoriasis | 90 mg

Crohn’s Disease and Ulcerative Colitis Initial Adult Intravenous Recommended Dosage (2.3): A single intravenous infusion using weight-based dosing:

Weight Range (kilograms) | Dose
up to 55 kg | 260 mg (2 vials)
greater than 55 kg to 85 kg | 390 mg (3 vials)
greater than 85 kg | 520 mg (4 vials)

Crohn’s Disease and Ulcerative Colitis Maintenance Adult Subcutaneous Recommended Dosage (2.3): A subcutaneous 90 mg dose 8 weeks after the initial intravenous dose, then every 8 weeks thereafter.

3 DOSAGE FORMS AND STRENGTHS

Subcutaneous Injection (3)

- Injection: 45 mg/0.5 mL or 90 mg/mL solution in a single-dose prefilled syringe
- Injection: 45 mg/0.5 mL solution in a single-dose vial

Intravenous Infusion (3)

- Injection: 130 mg/26 mL (5 mg/mL) solution in a single-dose vial (3)

4 CONTRAINDICATIONS

Clinically significant hypersensitivity to ustekinumab products or to any of the excipients in STARJEMZA. (4)

5 WARNINGS AND PRECAUTIONS

- Infections: Serious infections have occurred. Avoid starting STARJEMZA during any clinically important active infection. If a serious infection or clinically significant infection develops, discontinue STARJEMZA until the infection resolves. (5.1)
- Theoretical Risk for Particular Infections: Serious infections from mycobacteria, salmonella, and Bacillus Calmette-Guerin (BCG) vaccinations have been reported in patients genetically deficient in IL-12/IL-23. Consider diagnostic tests for these infections as dictated by clinical circumstances. (5.2)
- Tuberculosis (TB): Evaluate patients for TB prior to initiating treatment with STARJEMZA. Initiate treatment of latent TB before administering STARJEMZA. (5.3)
- Malignancies: Ustekinumab products may increase risk of malignancy. The safety of ustekinumab products in patients with a history of or a known malignancy has not been evaluated. (5.4)
- Hypersensitivity Reactions: If an anaphylactic or other clinically significant hypersensitivity reaction occurs, institute appropriate therapy and discontinue STARJEMZA. (5.5)
- Posterior Reversible Encephalopathy Syndrome (PRES): If PRES is suspected, treat promptly, and discontinue STARJEMZA. (5.6)
- Immunizations: Avoid use of live vaccines in patients during treatment with STARJEMZA. (5.7)
- Noninfectious Pneumonia: Cases of interstitial pneumonia, eosinophilic pneumonia, and cryptogenic organizing pneumonia have been reported during post-approval use of ustekinumab products. If diagnosis is confirmed, discontinue STARJEMZA and institute appropriate treatment. (5.8)

6 ADVERSE REACTIONS

Most common adverse reactions are:

- Psoriasis (≥3%): nasopharyngitis, upper respiratory tract infection, headache, and fatigue. (6.1)
- Crohn’s Disease, induction (≥3%): vomiting. (6.1)
- Crohn’s Disease, maintenance (≥3%): nasopharyngitis, injection site erythema, vulvovaginal candidiasis/mycotic infection, bronchitis, pruritus, urinary tract infection, and sinusitis. (6.1)
- Ulcerative colitis, induction (≥3%): nasopharyngitis (6.1)
- Ulcerative colitis, maintenance (≥3%): nasopharyngitis, headache, abdominal pain, influenza, fever, diarrhea, sinusitis, fatigue, and nausea (6.1)

To report SUSPECTED ADVERSE REACTIONS, contact Hikma Pharmaceuticals USA Inc. at 1-877-845-0689 or FDA at 1-800-FDA-1088 (1-800-332-1088) or www.fda.gov/medwatch.

See 17 for PATIENT COUNSELING INFORMATION and Medication Guide.

* Biosimilar means that the biological product is approved based on data demonstrating that it is highly similar to an FDA-approved biological product, known as a reference product, and that there are no clinically meaningful differences between the biosimilar product and the reference product. Biosimilarity of STARJEMZA has been demonstrated for the condition(s) of use (e.g., indication(s), dosing regimen(s)), strength(s), dosage form(s), and route(s) of administration described in its Full Prescribing Information.

FULL PRESCRIBING INFORMATION

1 INDICATIONS AND USAGE

1.1 Plaque Psoriasis (PsO)

STARJEMZA is indicated for the treatment of adults and pediatric patients 6 years of age and older with moderate to severe plaque psoriasis who are candidates for phototherapy or systemic therapy.

1.2 Psoriatic Arthritis (PsA)

STARJEMZA is indicated for the treatment of adults and pediatric patients 6 years of age and older with active psoriatic arthritis.

1.3 Crohn’s Disease (CD)

STARJEMZA is indicated for the treatment of adult patients with moderately to severely active Crohn’s disease.

1.4 Ulcerative Colitis

STARJEMZA is indicated for the treatment of adult patients with moderately to severely active ulcerative colitis.

2 DOSAGE AND ADMINISTRATION

2.1 Recommended Dosage in Plaque Psoriasis

Subcutaneous Adult Dosage Regimen

- For patients weighing 100 kg or less, the recommended dosage is 45 mg initially and 4 weeks later, followed by 45 mg every 12 weeks.
- For patients weighing more than 100 kg, the recommended dosage is 90 mg initially and 4 weeks later, followed by 90 mg every 12 weeks.

In subjects weighing more than 100 kg, 45 mg was also shown to be efficacious. However, 90 mg resulted in greater efficacy in these subjects [see Clinical Studies (14)].

Subcutaneous Pediatric Dosage Regimen

Administer STARJEMZA subcutaneously at Weeks 0 and 4, then every 12 weeks thereafter.

The recommended dose of STARJEMZA for pediatric patients (6-17 years old) with plaque psoriasis based on body weight is shown below (Table 1).

For pediatric patients weighing less than 60 kg, the administration volume for the recommended dose (0.75 mg/kg) is shown in Table 2; withdraw the appropriate volume from the single-dose vial.

2.2 Recommended Dosage in Psoriatic Arthritis

Subcutaneous Adult Dosage Regimen

- The recommended dosage is 45 mg initially and 4 weeks later, followed by 45 mg every 12 weeks.
- For patients with co-existent moderate-to-severe plaque psoriasis weighing more than 100 kg, the recommended dosage is 90 mg initially and 4 weeks later, followed by 90 mg every 12 weeks.

Subcutaneous Pediatric Dosage Regimen

Administer STARJEMZA subcutaneously at Weeks 0 and 4, then every 12 weeks thereafter.

The recommended dose of STARJEMZA for pediatric patients (6 to 17 years old) with psoriatic arthritis, based on body weight, is shown below (Table 3).

2.3 Recommended Dosage in Crohn’s Disease and Ulcerative Colitis

Intravenous Induction Adult Dosage Regimen

A single intravenous infusion dose of STARJEMZA using the weight-based dosage regimen specified in Table 4 [see Instructions for dilution of STARJEMZA 130 mg vial for intravenous infusion (2.6)].

Subcutaneous Maintenance Adult Dosage Regimen

The recommended maintenance dosage is a subcutaneous 90 mg dose administered 8 weeks after the initial intravenous dose, then every 8 weeks thereafter.

2.4 General Considerations for Administration

- STARJEMZA is intended for use under the guidance and supervision of a healthcare provider. STARJEMZA should only be administered to patients who will be closely monitored and have regular follow-up visits with a healthcare provider. The appropriate dose should be determined by a healthcare provider using the patient’s current weight at the time of dosing. In pediatric patients, it is recommended that STARJEMZA be administered by a healthcare provider. If a healthcare provider determines that it is appropriate, a patient may self-inject or a caregiver may inject STARJEMZA after proper training in subcutaneous injection technique. Instruct patients to follow the directions provided in the Medication Guide [see Medication Guide].
- The needle cover on the prefilled syringe contains dry natural rubber (a derivative of latex). The needle cover should not be handled by persons sensitive to latex.
- It is recommended that each injection be administered at a different anatomic location (such as upper arms, gluteal regions, thighs, or any quadrant of abdomen) than the previous injection, and not into areas where the skin is tender, bruised, erythematous, or indurated. When using the single-dose vial, a 1 mL syringe with a 27 gauge, 1/2 inch needle is recommended.
- Parenteral drug products should be inspected visually for particulate matter and discoloration prior to administration, whenever solution and container permit. STARJEMZA is a clear, colorless to light yellow solution. Do not use STARJEMZA if it is discolored or cloudy, or if other particulate matter is present. STARJEMZA does not contain preservatives; therefore, discard any unused product remaining in the vial and/or syringe.

2.5 Instructions for Administration of STARJEMZA Prefilled Syringes Equipped with Needle Safety Guard

Refer to the diagram below for the provided instructions.

- Hold the BODY and remove the NEEDLE COVER. Do not hold the PLUNGER or PLUNGER HEAD while removing the NEEDLE COVER or the PLUNGER may move. Do not use the prefilled syringe if it is dropped without the NEEDLE COVER in place.
- Inject STARJEMZA subcutaneously as recommended [see Dosage and Administration (2.1, 2.2, 2.3)].
- Inject all of the medication by pushing in the PLUNGER until the PLUNGER HEAD is completely between the needle guard wings. Injection of the entire prefilled syringe contents is necessary to activate the needle guard.

- After injection, maintain the pressure on the PLUNGER HEAD and remove the needle from the skin. Slowly take your thumb off the PLUNGER HEAD to allow the empty syringe to move up until the entire needle is covered by the needle guard, as shown by the illustration below:

- Used syringes should be placed in a puncture-resistant container.

2.6 Preparation and Administration of STARJEMZA 130 mg/26 mL (5 mg/mL) Vial for Intravenous Infusion (Crohn’s Disease and Ulcerative Colitis)

STARJEMZA solution for intravenous infusion must be diluted, prepared, and infused by a healthcare professional using aseptic technique.

1. Calculate the dose and the number of STARJEMZA vials needed based on patient weight (Table 4). Each 26 mL vial of STARJEMZA contains 130 mg of ustekinumab-hmny.
2. Withdraw, and then discard a volume of the 0.9% Sodium Chloride Injection, USP from the 250 mL infusion bag equal to the volume of STARJEMZA to be added (discard 26 mL sodium chloride for each vial of STARJEMZA needed, for 2 vials- discard 52 mL, for 3 vials- discard 78 mL, 4 vials- discard 104 mL).
3. Withdraw 26 mL of STARJEMZA from each vial needed and add it to the 250 mL infusion bag. The final volume in the infusion bag should be 250 mL. Gently mix.
4. Visually inspect the diluted solution before infusion. Do not use if visibly opaque particles, discoloration or foreign particles are observed.
5. Infuse the diluted solution over a period of at least one hour. Once diluted, the infusion should be completely administered within eight hours of the dilution in the infusion bag.
6. Use only an infusion set with an in-line, sterile, non-pyrogenic, low protein-binding filter (pore size 0.2 micrometer).
7. Do not infuse STARJEMZA concomitantly in the same intravenous line with other agents.
8. STARJEMZA does not contain preservatives. Each vial is for one-time use in only one patient. Discard any remaining solution. Dispose any unused medicinal product in accordance with local requirements.

Storage

If necessary, the diluted infusion solution may be kept at room temperature up to 25°C (77°F) for up to 7 hours. Storage time at room temperature begins once the diluted solution has been prepared. The infusion should be completed within 8 hours after the dilution in the infusion bag (cumulative time after preparation including the storage and the infusion period). Do not freeze. Discard any unused portion of the infusion solution.

3 DOSAGE FORMS AND STRENGTHS

STARJEMZA™ (ustekinumab-hmny) is a clear, colorless to light yellow solution.

Subcutaneous Injection

- Injection: 45 mg/0.5 mL or 90 mg/mL solution in a single-dose prefilled syringe
- Injection: 45 mg/0.5 mL solution in a single-dose vial

Intravenous Infusion

- Injection: 130 mg/26 mL (5 mg/mL) solution in a single-dose vial

4 CONTRAINDICATIONS

STARJEMZA is contraindicated in patients with clinically significant hypersensitivity to ustekinumab products or to any of the excipients in STARJEMZA [see Warnings and Precautions (5.5)].

5 WARNINGS AND PRECAUTIONS

5.1 Infections

Ustekinumab products may increase the risk of infections and reactivation of latent infections. Serious bacterial, mycobacterial, fungal, and viral infections were observed in patients receiving ustekinumab products [see Adverse Reactions (6.1, 6.3)].

Serious infections requiring hospitalization, or otherwise clinically significant infections, reported in clinical trials included the following:

- Plaque Psoriasis: diverticulitis, cellulitis, pneumonia, appendicitis, cholecystitis, sepsis, osteomyelitis, viral infections, gastroenteritis, and urinary tract infections.
- Psoriatic arthritis: cholecystitis.
- Crohn’s disease: anal abscess, gastroenteritis, ophthalmic herpes zoster, pneumonia, and listeria meningitis.
- Ulcerative colitis: gastroenteritis, ophthalmic herpes zoster, pneumonia, and listeriosis.

Avoid initiating treatment with STARJEMZA in patients with any clinically important active infection until the infection resolves or is adequately treated. Consider the risks and benefits of treatment prior to initiating use of STARJEMZA in patients with a chronic infection or a history of recurrent infection.

Instruct patients to seek medical advice if signs or symptoms suggestive of an infection occur while on treatment with STARJEMZA and discontinue STARJEMZA for serious or clinically significant infections until the infection resolves or is adequately treated.

5.2 Theoretical Risk for Vulnerability to Particular Infections

Individuals genetically deficient in IL-12/IL-23 are particularly vulnerable to disseminated infections from mycobacteria (including nontuberculous, environmental mycobacteria), salmonella (including nontyphi strains), and Bacillus Calmette-Guerin (BCG) vaccinations. Serious infections and fatal outcomes have been reported in such patients.

It is not known whether patients with pharmacologic blockade of IL-12/IL-23 from treatment with ustekinumab products may be susceptible to these types of infections. Consider appropriate diagnostic testing, (e.g., tissue culture, stool culture, as dictated by clinical circumstances).

5.3 Pre-treatment Evaluation for Tuberculosis

Evaluate patients for tuberculosis infection prior to initiating treatment with STARJEMZA.

Avoid administering STARJEMZA to patients with active tuberculosis infection. Initiate treatment of latent tuberculosis prior to administering STARJEMZA. Consider anti-tuberculosis therapy prior to initiation of STARJEMZA in patients with a past history of latent or active tuberculosis in whom an adequate course of treatment cannot be confirmed. Closely monitor patients receiving STARJEMZA for signs and symptoms of active tuberculosis during and after treatment.

5.4 Malignancies

Ustekinumab products are immunosuppressants and may increase the risk of malignancy. Malignancies were reported among subjects who received ustekinumab in clinical trials [see Adverse Reactions (6.1)]. In rodent models, inhibition of IL-12/IL-23p40 increased the risk of malignancy [see Nonclinical Toxicology (13)].

The safety of ustekinumab products has not been evaluated in patients who have a history of malignancy or who have a known malignancy.

There have been post-marketing reports of the rapid appearance of multiple cutaneous squamous cell carcinomas in patients receiving ustekinumab products who had pre-existing risk factors for developing non-melanoma skin cancer. Monitor all patients receiving STARJEMZA for the appearance of non-melanoma skin cancer. Closely follow patients greater than 60 years of age, those with a medical history of prolonged immunosuppressant therapy and those with a history of PUVA treatment [see Adverse Reactions (6.1)].

5.5 Hypersensitivity Reactions

Hypersensitivity reactions, including anaphylaxis and angioedema, have been reported with ustekinumab products [see Adverse Reactions (6.1, 6.3)]. If an anaphylactic or other clinically significant hypersensitivity reaction occurs, institute appropriate therapy and discontinue STARJEMZA.

5.6 Posterior Reversible Encephalopathy Syndrome (PRES)

Two cases of posterior reversible encephalopathy syndrome (PRES), also known as Reversible Posterior Leukoencephalopathy Syndrome (RPLS), were reported in clinical trials. Cases have also been reported in postmarketing experience in patients with psoriasis, psoriatic arthritis, and Crohn’s disease. Clinical presentation included headaches, seizures, confusion, visual disturbances, and imaging changes consistent with PRES a few days to several months after ustekinumab product initiation. A few cases reported latency of a year or longer. Patients recovered with supportive care following withdrawal of ustekinumab products.

Monitor all patients treated with STARJEMZA for signs and symptoms of PRES. If PRES is suspected, promptly administer appropriate treatment and discontinue STARJEMZA.

5.7 Immunizations

Prior to initiating therapy with STARJEMZA, patients should receive all age-appropriate immunizations as recommended by current immunization guidelines. Patients being treated with STARJEMZA should avoid receiving live vaccines. Avoid administering BCG vaccines during treatment with STARJEMZA or for one year prior to initiating treatment or one year following discontinuation of treatment. Caution is advised when administering live vaccines to household contacts of patients receiving STARJEMZA because of the potential risk for shedding from the household contact and transmission to patient.

Non-live vaccinations received during a course of STARJEMZA may not elicit an immune response sufficient to prevent disease.

5.8 Noninfectious Pneumonia

Cases of interstitial pneumonia, eosinophilic pneumonia, and cryptogenic organizing pneumonia have been reported during post-approval use of ustekinumab products. Clinical presentations included cough, dyspnea, and interstitial infiltrates following one to three doses. Serious outcomes have included respiratory failure and prolonged hospitalization. Patients improved with discontinuation of therapy and in certain cases administration of corticosteroids. If diagnosis is confirmed, discontinue STARJEMZA and institute appropriate treatment [see Postmarketing Experience (6.3)].

6 ADVERSE REACTIONS

The following serious adverse reactions are discussed elsewhere in the label:

- Infections [see Warnings and Precautions (5.1)]
- Malignancies [see Warnings and Precautions (5.4)]
- Hypersensitivity Reactions [see Warnings and Precautions (5.5)]
- Posterior Reversible Encephalopathy Syndrome (PRES) [see Warnings and Precautions (5.6)]
- Noninfectious Pneumonia [see Warnings and Precautions (5.8)]

6.1 Clinical Trials Experience

Because clinical trials are conducted under widely varying conditions, adverse reaction rates observed in the clinical trials of a drug cannot be directly compared to rates in the clinical trials of another drug and may not reflect the rates observed in practice.

Adult Subjects with Plaque Psoriasis

The safety data reflect exposure to ustekinumab in 3117 adult subjects with plaque psoriasis, including 2414 exposed for at least 6 months, 1855 exposed for at least one year, 1653 exposed for at least two years, 1569 exposed for at least three years, 1482 exposed for at least four years and 838 exposed for at least five years.

Table 5 summarizes the adverse reactions that occurred at a rate of at least 1% with higher rates in the ustekinumab groups during the placebo-controlled period of Ps STUDY 1 and Ps STUDY 2 [see Clinical Studies (14)].

Adverse reactions that occurred at rates less than 1% in the controlled period of Ps STUDIES 1 and 2 through week 12 included: cellulitis, herpes zoster, diverticulitis, and certain injection site reactions (pain, swelling, pruritus, induration, hemorrhage, bruising, and irritation).

One case of PRES occurred during adult plaque psoriasis clinical trials [see Warnings and Precautions (5.6)].

Infections

In the placebo-controlled period of clinical trials of subjects with plaque psoriasis (average follow-up of 12.6 weeks for placebo-treated subjects and 13.4 weeks for ustekinumab-treated subjects), 27% of ustekinumab-treated subjects reported infections (1.39 per patient-years of follow-up) compared with 24% of placebo-treated subjects (1.21 per patient-years of follow-up). Serious infections occurred in 0.3% of ustekinumab-treated subjects (0.01 per patient-years of follow-up) and in 0.4% of placebo-treated subjects (0.02 per patient-years of follow-up) [see Warnings and Precautions (5.1)].

In the controlled and non-controlled portions of plaque psoriasis clinical trials (median follow-up of 3.2 years), representing 8998 patient-years of exposure, 72.3% of ustekinumab-treated subjects reported infections (0.87 per patient-years of follow-up). Serious infections were reported in 2.8% of subjects (0.01 per patient-years of follow-up).

Malignancies

In the controlled and non-controlled portions of plaque psoriasis clinical trials (median follow-up of 3.2 years, representing 8998 patient-years of exposure), 1.7% of ustekinumab-treated subjects reported malignancies excluding non-melanoma skin cancers (0.60 per hundred patient-years of follow-up). Non-melanoma skin cancer was reported in 1.5% of ustekinumab-treated subjects (0.52 per hundred patient-years of follow-up) [see Warnings and Precautions (5.4)]. The most frequently observed malignancies other than non-melanoma skin cancer during the clinical trials were: prostate, melanoma, colorectal and breast. Malignancies other than non-melanoma skin cancer in ustekinumab-treated subjects during the controlled and uncontrolled portions of trials were similar in type and number to what would be expected in the general U.S. population according to the SEER database (adjusted for age, gender and race).^1

Pediatric Subjects with Plaque Psoriasis

The safety of ustekinumab was assessed in two trials of pediatric subjects with moderate to severe plaque psoriasis. Ps STUDY 3 evaluated safety for up to 60 weeks in 110 pediatric subjects 12 to 17 years old. Ps STUDY 4 evaluated safety for up to 56 weeks in 44 pediatric subjects 6 to 11 years old. The safety profile in pediatric subjects was similar to the safety profile from trials in adults with plaque psoriasis.

Psoriatic Arthritis

The safety of ustekinumab was assessed in 927 subjects in two randomized, double-blind, placebo-controlled trials in adults with active psoriatic arthritis (PsA). The overall safety profile of ustekinumab in subjects with PsA was consistent with the safety profile seen in adult psoriasis clinical trials. A higher incidence of arthralgia, nausea, and dental infections was observed in ustekinumab-treated subjects when compared with placebo-treated subjects (3% vs. 1% for arthralgia and 3% vs. 1% for nausea; 1% vs. 0.6% for dental infections) in the placebo-controlled portions of the PsA clinical trials.

Crohn’s Disease

The safety of ustekinumab was assessed in 1407 subjects with moderately to severely active Crohn’s disease (Crohn’s Disease Activity Index [CDAI] greater than or equal to 220 and less than or equal to 450) in three randomized, double-blind, placebo-controlled, parallel-group, multicenter trials. These 1407 subjects included 40 subjects who received a prior investigational intravenous ustekinumab formulation but were not included in the efficacy analyses. In trials CD-1 and CD-2 there were 470 subjects who received ustekinumab 6 mg/kg as a weight-based single intravenous induction dose and 466 who received placebo [see Dosage and Administration (2.3)]. Subjects who were responders in either trial CD-1 or CD-2 were randomized to receive a subcutaneous maintenance regimen of either 90 mg ustekinumab every 8 weeks, or placebo for 44 weeks in trial CD-3. Subjects in these 3 trials may have received other concomitant therapies including aminosalicylates, immunomodulatory agents [azathioprine (AZA), 6-mercaptopurine (6-MP), methotrexate (MTX)], oral corticosteroids (prednisone or budesonide), and/or antibiotics for their Crohn’s disease [see Clinical Studies (14.4)].

The overall safety profile of ustekinumab was consistent with the safety profile seen in the adult psoriasis and psoriatic arthritis clinical trials. Common adverse reactions in trials CD-1 and CD-2 and in trial CD-3 are listed in Tables 6 and 7, respectively.

Other less common adverse reactions reported in subjects in trials CD-1 and CD-2 included asthenia (1% vs 0.4%), acne (1% vs 0.4%), and pruritus (2% vs 0.4%).

Infections

In subjects with Crohn’s disease, serious or other clinically significant infections included anal abscess, gastroenteritis, and pneumonia. In addition, listeria meningitis and ophthalmic herpes zoster were reported in one patient each [see Warnings and Precautions (5.1)].

Malignancies

With up to one year of treatment in the Crohn’s disease clinical trials, 0.2% of ustekinumab-treated subjects (0.36 events per hundred patient-years) and 0.2% of placebo-treated subjects (0.58 events per hundred patient-years) developed non-melanoma skin cancer. Malignancies other than non-melanoma skin cancers occurred in 0.2% of ustekinumab-treated subjects (0.27 events per hundred patient-years) and in none of the placebo-treated subjects.

Hypersensitivity Reactions Including Anaphylaxis

In CD trials, two subjects reported hypersensitivity reactions following ustekinumab administration. One patient experienced signs and symptoms consistent with anaphylaxis (tightness of the throat, shortness of breath, and flushing) after a single subcutaneous administration (0.1% of subjects receiving subcutaneous ustekinumab). In addition, one subject experienced signs and symptoms consistent with or related to a hypersensitivity reaction (chest discomfort, flushing, urticaria, and increased body temperature) after the initial intravenous ustekinumab dose (0.08% of subjects receiving intravenous ustekinumab). These subjects were treated with oral antihistamines or corticosteroids and in both cases symptoms resolved within an hour.

Ulcerative Colitis

The safety of ustekinumab was evaluated in two randomized, double-blind, placebo-controlled clinical trials (UC-1 [IV induction] and UC-2 [SC maintenance]) in 960 adult subjects with moderately to severely active ulcerative colitis [see Clinical Studies (14.5)]. The overall safety profile of ustekinumab in subjects with ulcerative colitis was consistent with the safety profile seen across all approved indications. Adverse reactions reported in at least 3% of ustekinumab-treated subjects and at a higher rate than placebo were:

- Induction (UC-1): nasopharyngitis (7% vs 4%).
- Maintenance (UC-2): nasopharyngitis (24% vs 20%), headache (10% vs 4%), abdominal pain (7% vs 3%), influenza (6% vs 5%), fever (5% vs. 4%), diarrhea (4% vs 1%), sinusitis (4% vs 1%), fatigue (4% vs 2%), and nausea (3% vs 2%).

Infections

In subjects with ulcerative colitis, serious or other clinically significant infections included gastroenteritis and pneumonia. In addition, listeriosis and ophthalmic herpes zoster were reported in one subject each [see Warnings and Precautions (5.1)].

Malignancies

With up to one year of treatment in the ulcerative colitis clinical trials, 0.4% of ustekinumab-treated subjects (0.48 events per hundred patient-years) and 0.0% of placebo-treated subjects (0.00 events per hundred patient-years) developed non-melanoma skin cancer. Malignancies other than non-melanoma skin cancers occurred in 0.5% of ustekinumab-treated subjects (0.64 events per hundred patient-years) and 0.2% of placebo-treated subjects (0.40 events per hundred patient-years).

6.2 Immunogenicity

The observed incidence of anti-drug antibodies is highly dependent on the sensitivity and specificity of the assay. Differences in assay methods preclude meaningful comparisons of the incidence of anti-drug antibodies in the studies described below with the incidence of anti-drug antibodies in other studies, including those of ustekinumab or of other ustekinumab products.

Approximately 6 to 12.4% of subjects treated with ustekinumab in plaque psoriasis and psoriatic arthritis clinical trials developed antibodies to ustekinumab, which were generally low-titer. In plaque psoriasis clinical trials, antibodies to ustekinumab were associated with reduced or undetectable serum ustekinumab concentrations and reduced efficacy. In plaque psoriasis trials, the majority of subjects who were positive for antibodies to ustekinumab had neutralizing antibodies.

In Crohn’s disease and ulcerative colitis clinical trials, 2.9% and 4.6% of subjects, respectively, developed antibodies to ustekinumab when treated with ustekinumab for approximately one year. No apparent association between the development of antibodies to ustekinumab and the development of injection site reactions was seen.

6.3 Postmarketing Experience

The following adverse reactions have been reported during post-approval use of ustekinumab products. Because these reactions are reported voluntarily from a population of uncertain size, it is not always possible to reliably estimate their frequency or establish a causal relationship to ustekinumab product exposure.

Immune system disorders: Serious hypersensitivity reactions (including anaphylaxis and angioedema), other hypersensitivity reactions (including rash and urticaria).

Infections and infestations: Lower respiratory tract infection (including opportunistic fungal infections and tuberculosis).

Neurological disorders: Posterior Reversible Encephalopathy Syndrome (PRES).

Respiratory, thoracic, and mediastinal disorders: Interstitial pneumonia, eosinophilic pneumonia, and cryptogenic organizing pneumonia.

Skin reactions: Pustular psoriasis, erythrodermic psoriasis, hypersensitivity vasculitis.

7 DRUG INTERACTIONS

7.1 Concomitant Therapies

In plaque psoriasis trials the safety of ustekinumab products in combination with immunosuppressive agents or phototherapy has not been evaluated. In psoriatic arthritis trials, concomitant MTX use did not appear to influence the safety or efficacy of ustekinumab. In Crohn’s disease and ulcerative colitis induction trials, immunomodulators (6-MP, AZA, MTX) were used concomitantly in approximately 30% of subjects and corticosteroids were used concomitantly in approximately 40% and 50% of Crohn’s disease and ulcerative colitis subjects, respectively. Use of these concomitant therapies did not appear to influence the overall safety or efficacy of ustekinumab.

7.2 CYP450 Substrates

The formation of CYP450 enzymes can be suppressed by increased levels of certain cytokines (e.g., IL-1, IL-6, TNFα, IFN) during chronic inflammation. Thus, use of ustekinumab products, antagonists of IL-12 and IL-23, could normalize the formation of CYP450 enzymes. Upon initiation or discontinuation of STARJEMZA in patients who are receiving concomitant CYP450 substrates, particularly those with a narrow therapeutic index, consider monitoring for therapeutic effect or drug concentration and adjust the individual dosage of the CYP substrate as needed. See the prescribing information of specific CYP substrates.

A CYP-mediated drug interaction effect was not observed in subjects with Crohn’s disease [see Clinical Pharmacology (12.3)].

7.3 Allergen Immunotherapy

Ustekinumab products have not been evaluated in patients who have undergone allergy immunotherapy. Ustekinumab products may decrease the protective effect of allergen immunotherapy (decrease tolerance) which may increase the risk of an allergic reaction to a dose of allergen immunotherapy. Therefore, caution should be exercised in patients receiving or who have received allergen immunotherapy, particularly for anaphylaxis.

8 USE IN SPECIFIC POPULATIONS

8.1 Pregnancy

Risk Summary

Limited data from observational studies, published case reports, and postmarketing surveillance on the use of ustekinumab products during pregnancy are insufficient to inform a drug associated risk of major birth defects, miscarriage, and other adverse maternal or fetal outcomes. Transport of human IgG antibody across the placenta increases as pregnancy progresses and peaks during the third trimester; therefore, ustekinumab products may be transferred to the developing fetus [see Clinical Considerations]. In animal reproductive and developmental toxicity studies, no adverse developmental effects were observed in offspring after administration of ustekinumab to pregnant monkeys at exposures greater than 100 times the maximum recommended human dose (MRHD).

The background risk of major birth defects and miscarriage for the indicated population(s) are unknown. All pregnancies have a background risk of birth defect, loss, or other adverse outcomes. In the U.S. general population, the estimated background risk of major birth defects and miscarriage of clinically recognized pregnancies is 2% to 4% and 15% to 20%, respectively.

Clinical Considerations

Fetal/Neonatal Adverse Reactions

Because ustekinumab products may theoretically interfere with immune response to infections, consider risks and benefits prior to administering live vaccines to infants exposed to STARJEMZA in utero. There are insufficient data regarding exposed infant serum levels of ustekinumab products at birth and the duration of persistence of ustekinumab products in infant serum after birth. Although a specific timeframe to delay administration of live attenuated vaccines in infants exposed in utero is unknown, consider the risks and benefits of delaying a minimum of 6 months after birth because of the clearance of the product.

Data

Animal Data

Ustekinumab was tested in two embryo-fetal development toxicity studies in cynomolgus monkeys. No teratogenic or other adverse developmental effects were observed in fetuses from pregnant monkeys that were administered ustekinumab subcutaneously twice weekly or intravenously weekly during the period of organogenesis. Serum concentrations of ustekinumab in pregnant monkeys were greater than 100 times the serum concentration in patients treated subcutaneously with 90 mg of ustekinumab weekly for 4 weeks.

In a combined embryo-fetal development and pre- and post-natal development toxicity study, pregnant cynomolgus monkeys were administered subcutaneous doses of ustekinumab twice weekly at exposures greater than 100 times the MRHD from the beginning of organogenesis to Day 33 after delivery. Neonatal deaths occurred in the offspring of one monkey administered ustekinumab at 22.5 mg/kg and one monkey dosed at 45 mg/kg. No ustekinumab-related- effects on functional, morphological, or immunological development were observed in the neonates from birth through six months of age.

8.2 Lactation

Risk Summary

Limited data from published literature suggests that ustekinumab is present in human breast milk. There are no available data on the effects of ustekinumab products on milk production. The effects of local gastrointestinal exposure and limited systemic exposure in the breastfed infant to ustekinumab products are unknown. No adverse effects on the breastfed infant causally related to ustekinumab products have been identified in the published literature or postmarketing experience.

The developmental and health benefits of breastfeeding should be considered along with the mother’s clinical need for STARJEMZA and any potential adverse effects on the breastfed child from STARJEMZA or from the underlying maternal condition.

8.4 Pediatric Use

Plaque Psoriasis

The safety and effectiveness of STARJEMZA have been established for the treatment of moderate to severe plaque psoriasis in pediatric patients 6 to 17 years of age who are candidates for phototherapy or systemic therapy.

Use of STARJEMZA in pediatric patients 12 to less than 17 years of age is supported by evidence from a multicenter, randomized, 60-week trial (Ps STUDY 3) of ustekinumab that included a 12-week, double-blind, placebo-controlled, parallel group portion, in 110 pediatric subjects 12 years of age and older [see Adverse Reactions (6.1), Clinical Studies (14.2)].

Use of STARJEMZA in pediatric patients 6 to 11 years of age is supported by evidence from an open-label, single-arm, efficacy, safety, and pharmacokinetics trial (Ps STUDY 4) of ustekinumab in 44 subjects [see Adverse Reactions (6.1), Pharmacokinetics (12.3)].

The safety and effectiveness of STARJEMZA have not been established in pediatric patients less than 6 years of age with plaque psoriasis.

Psoriatic Arthritis

The safety and effectiveness of STARJEMZA have been established for treatment of psoriatic arthritis in pediatric patients 6 to 17 years old.

Use of STARJEMZA in these age groups is supported by evidence from adequate and well controlled trials of ustekinumab in adults with psoriasis and PsA, pharmacokinetic data from adult subjects with psoriasis, adult subjects with PsA and pediatric subjects with psoriasis, and safety data of ustekinumab from two clinical trials in 44 pediatric subjects 6 to 11 years old with psoriasis and 110 pediatric subjects 12 to 17 years old with psoriasis. The observed pre-dose (trough) concentrations are generally comparable between adult subjects with psoriasis, adult subjects with PsA and pediatric subjects with psoriasis, and the PK exposure is expected to be comparable between adult and pediatric subjects with PsA [see Adverse Reactions (6.1), Clinical Pharmacology (12.3), and Clinical Studies (14.1, 14.2, 14.3)].

The safety and effectiveness of STARJEMZA have not been established in pediatric patients less than 6 years old with psoriatic arthritis.

Crohn’s Disease and Ulcerative Colitis

The safety and effectiveness of STARJEMZA have not been established in pediatric patients with Crohn’s disease or ulcerative colitis.

8.5 Geriatric Use

Of the 6709 subjects exposed to ustekinumab, a total of 340 were 65 years of age or older (183 subjects with plaque psoriasis, 65 subjects with psoriatic arthritis, 58 subjects with Crohn’s disease, and 34 subjects with ulcerative colitis), and 40 subjects were 75 years of age or older. Clinical trials of ustekinumab did not include sufficient numbers of subjects 65 years of age and older to determine whether they respond differently from younger adult subjects.

10 OVERDOSAGE

Single doses up to 6 mg/kg intravenously have been administered in clinical trials without dose-limiting toxicity. In case of overdosage, monitor the patient for any signs or symptoms of adverse reactions or effects and institute appropriate symptomatic treatment immediately. Consider contacting the Poison Help line (1-800-222-1222) or a medical toxicologist for additional overdose management recommendations.

11 DESCRIPTION

Ustekinumab-hmny, a human IgG1κ monoclonal antibody, is a human interleukin-12 and -23 antagonist. Using DNA recombinant technology, ustekinumab-hmny is produced in a Chinese hamster ovary cell line (CHO-BAT). The manufacturing process contains steps for the clearance of viruses. Ustekinumab-hmny is comprised of 1326 amino acids and has an estimated molecular mass of approximately 145,000 Daltons (the polypeptide part only).

STARJEMZA™ (ustekinumab-hmny) injection is a sterile, preservative-free, clear, colorless to light yellow solution with pH of 5.7-6.3.

STARJEMZA for Subcutaneous Use

Available as 45 mg of ustekinumab-hmny in 0.5 mL and 90 mg of ustekinumab-hmny in 1 mL, supplied as a sterile solution in a single-dose prefilled syringe with a 27 gauge fixed 1/2 inch needle and as 45 mg of ustekinumab-hmny in 0.5 mL in a single-dose 2 mL Type I glass vial with a coated stopper. The syringe is fitted with a passive needle guard and a needle cover that contains dry natural rubber (a derivative of latex).

Each 0.5 mL prefilled syringe or vial delivers 45 mg ustekinumab-hmny, histidine (0.265 mg), L-histidine hydrochloride monohydrate (0.685 mg), polysorbate 80 (0.05 mg), and sucrose (38 mg).

Each 1 mL prefilled syringe delivers 90 mg ustekinumab-hmny, histidine (0.53 mg), L-histidine hydrochloride monohydrate (1.37 mg), polysorbate 80 (0.1 mg), and sucrose (76 mg).

STARJEMZA for Intravenous Infusion

Available as 130 mg of ustekinumab-hmny in 26 mL, supplied as a single-dose 30 mL Type I glass vial with a coated stopper.

Each 26 mL vial delivers 130 mg ustekinumab-hmny, edetate disodium (0.52 mg), histidine (20 mg), L-histidine hydrochloride monohydrate (27 mg), methionine (10.4 mg), polysorbate 80 (10.4 mg), and sucrose (2210 mg).

12 CLINICAL PHARMACOLOGY

12.1 Mechanism of Action

Ustekinumab products are human IgG1қ monoclonal antibodies that bind with specificity to the p40 protein subunit used by both the IL-12 and IL-23 cytokines. IL-12 and IL-23 are naturally occurring cytokines that are involved in inflammatory and immune responses, such as natural killer cell activation and CD4+ T-cell differentiation and activation. In in vitro models, ustekinumab products were shown to disrupt IL-12 and IL-23 mediated signaling and cytokine cascades by disrupting the interaction of these cytokines with a shared cell-surface receptor chain, IL-12Rβ1. The cytokines IL-12 and IL-23 have been implicated as important contributors to the chronic inflammation that is a hallmark of Crohn’s disease and ulcerative colitis. In animal models of colitis, genetic absence or antibody blockade of the p40 subunit of IL-12 and IL-23, the target of ustekinumab products, was shown to be protective.

12.2 Pharmacodynamics

Plaque Psoriasis

In a small exploratory trial, a decrease was observed in the expression of mRNA of its molecular targets IL-12 and IL-23 in lesional skin biopsies measured at baseline and up to two weeks post-treatment in subjects with plaque psoriasis.

Ulcerative Colitis

In both trial UC-1 (induction) and trial UC-2 (maintenance), a positive relationship was observed between exposure and rates of clinical remission, clinical response, and endoscopic improvement. The response rate approached a plateau at the ustekinumab exposures associated with the recommended dosing regimen for maintenance treatment [see Clinical Studies (14.5)].

12.3 Pharmacokinetics

Absorption

In adult subjects with plaque psoriasis, the median time to reach the maximum serum concentration (Tmax) was 13.5 days and 7 days, respectively, after a single subcutaneous administration of 45 mg (N=22) and 90 mg (N=24) of ustekinumab. In healthy subjects (N=30), the median Tmax value (8.5 days) following a single subcutaneous administration of 90 mg of ustekinumab was comparable to that observed in subjects with plaque psoriasis.

Following multiple subcutaneous doses of ustekinumab in adult subjects with plaque psoriasis, steady-state serum concentrations of ustekinumab were achieved by Week 28. The mean (±SD) steady-state trough serum ustekinumab concentrations were 0.69 ± 0.69 mcg/mL for subjects less than or equal to 100 kg receiving a 45 mg dose and 0.74 ± 0.78 mcg/mL for subjects greater than 100 kg receiving a 90 mg dose. There was no apparent accumulation in serum ustekinumab concentration over time when given subcutaneously every 12 weeks.

Following the recommended intravenous induction dose, mean ±SD peak serum ustekinumab concentration was 125.2 ± 33.6 mcg/mL in subjects with Crohn’s disease, and 129.1 ± 27.6 mcg/mL in subjects with ulcerative colitis. Starting at Week 8, the recommended subcutaneous maintenance dosing of 90 mg ustekinumab was administered every 8 weeks. Steady state ustekinumab concentration was achieved by the start of the second maintenance dose. There was no apparent accumulation in ustekinumab concentration over time when given subcutaneously every 8 weeks. Mean ±SD steady-state trough concentration was 2.5 ± 2.1 mcg/mL in subjects with Crohn’s disease, and 3.3 ± 2.3 mcg/mL in subjects with ulcerative colitis for 90 mg ustekinumab administered every 8 weeks.

Distribution

Population pharmacokinetic analyses showed that the volume of distribution of ustekinumab in the central compartment was 2.7 L (95% CI: 2.69, 2.78) in subjects with Crohn’s disease and 3.0 L (95% CI: 2.96, 3.07) in subjects with ulcerative colitis. The total volume of distribution at steady-state was 4.6 L in subjects with Crohn’s disease and 4.4 L in subjects with ulcerative colitis.

Elimination

The mean (±SD) half-life ranged from 14.9 ± 4.6 to 45.6 ± 80.2 days across all plaque psoriasis trials following subcutaneous administration. Population pharmacokinetic analyses showed that the clearance of ustekinumab was 0.19 L/day (95% CI: 0.185, 0.197) in subjects with Crohn’s disease and 0.19 L/day (95% CI: 0.179, 0.192) in subjects with ulcerative colitis with an estimated median terminal half-life of approximately 19 days for both IBD (Crohn’s disease and ulcerative colitis) populations.

These results indicate the pharmacokinetics of ustekinumab were similar between subjects with Crohn’s disease and ulcerative colitis.

Metabolism

The metabolic pathway of ustekinumab products have not been characterized. As a human IgG1κ monoclonal antibody, ustekinumab products are expected to be degraded into small peptides and amino acids via catabolic pathways in the same manner as endogenous IgG.

Specific Populations

Weight

When given the same dose, subjects with plaque psoriasis or psoriatic arthritis weighing more than 100 kg had lower median serum ustekinumab concentrations compared with those subjects weighing 100 kg or less. The median trough serum concentrations of ustekinumab in subjects of higher weight (greater than 100 kg) in the 90 mg group were comparable to those in subjects of lower weight (100 kg or less) in the 45 mg group.

Age: Geriatric Population

A population pharmacokinetic analysis (N=106/1937 subjects with plaque psoriasis greater than or equal to 65 years old) was performed to evaluate the effect of age on the pharmacokinetics of ustekinumab. There were no apparent changes in pharmacokinetic parameters (clearance and volume of distribution) in subjects older than 65 years old.

Age: Pediatric Population

Following multiple recommended doses of ustekinumab in pediatric subjects 6 to 17 years of age with plaque psoriasis, steady-state serum concentrations of ustekinumab were achieved by Week 28. At Week 28, the mean ±SD steady-state trough serum ustekinumab concentrations were 0.36 ± 0.26 mcg/mL and 0.54 ± 0.43 mcg/mL, respectively, in pediatric subjects 6 to 11 years of age and pediatric subjects 12 to 17 years of age.

Overall, the observed steady-state ustekinumab trough concentrations in pediatric subjects with plaque psoriasis were within the range of those observed for adult subjects with plaque psoriasis and adult subjects with PsA after administration of ustekinumab.

Drug Interaction Studies

The effects of IL-12 or IL-23 on the regulation of CYP450 enzymes were evaluated in an in vitro study using human hepatocytes, which showed that IL-12 and/or IL-23 at levels of 10 ng/mL did not alter human CYP450 enzyme activities (CYP1A2, 2B6, 2C9, 2C19, 2D6, or 3A4).

No clinically significant changes in exposure of caffeine (CYP1A2 substrate), warfarin (CYP2C9 substrate), omeprazole (CYP2C19 substrate), dextromethorphan (CYP2D6 substrate), or midazolam (CYP3A substrate) were observed when used concomitantly with ustekinumab at the approved recommended dosage in subjects with Crohn’s disease [see Drug Interactions (7.2)].

Population pharmacokinetic analyses indicated that the clearance of ustekinumab was not impacted by concomitant MTX, NSAIDs, and oral corticosteroids, or prior exposure to a TNF blocker in subjects with psoriatic arthritis.

In subjects with Crohn’s disease and ulcerative colitis, population pharmacokinetic analyses did not indicate changes in ustekinumab clearance with concomitant use of corticosteroids or immunomodulators (AZA, 6-MP, or MTX); and serum ustekinumab concentrations were not impacted by concomitant use of these medications.

13 NONCLINICAL TOXICOLOGY

13.1 Carcinogenesis, Mutagenesis, Impairment of Fertility

Animal studies have not been conducted to evaluate the carcinogenic or mutagenic potential of ustekinumab products. Published literature showed that administration of murine IL-12 caused an anti-tumor effect in mice that contained transplanted tumors and IL-12/IL-23p40 knockout mice or mice treated with anti-IL-12/IL-23p40 antibody had decreased host defense to tumors. Mice genetically manipulated to be deficient in both IL-12 and IL-23 or IL-12 alone developed UV- induced skin cancers earlier and more frequently compared to wild-type mice. The relevance of these experimental findings in mouse models for malignancy risk in humans is unknown.

No effects on fertility were observed in male cynomolgus monkeys that were administered ustekinumab at subcutaneous doses up to 45 mg/kg twice weekly (45 times the MRHD on a mg/kg basis) prior to and during the mating period. However, fertility and pregnancy outcomes were not evaluated in mated females.

No effects on fertility were observed in female mice that were administered an analogous IL-12/IL- 23p40 antibody by subcutaneous administration at doses up to 50 mg/kg, twice weekly, prior to and during early pregnancy.

13.2 Animal Toxicology and/or Pharmacology

In a 26-week toxicology study, one out of 10 monkeys subcutaneously administered 45 mg/kg ustekinumab twice weekly for 26 weeks had a bacterial infection.

14 CLINICAL STUDIES

14.1 Adult Plaque Psoriasis

Two multicenter, randomized, double-blind, placebo-controlled trials (Ps STUDY 1 and Ps STUDY 2) enrolled a total of 1996 subjects 18 years of age and older with plaque psoriasis who had a minimum body surface area involvement of 10%, and Psoriasis Area and Severity Index (PASI) score ≥12, and who were candidates for phototherapy or systemic therapy. Subjects with guttate, erythrodermic, or pustular psoriasis were excluded from the trials.

Ps STUDY 1 enrolled 766 subjects and Ps STUDY 2 enrolled 1230 subjects. The trials had the same design through Week 28. In both trials, subjects were randomized in equal proportion to

placebo, 45 mg or 90 mg of ustekinumab. Subjects randomized to ustekinumab received 45 mg or 90 mg doses, regardless of weight, at Weeks 0, 4, and 16. Subjects randomized to receive placebo at Weeks 0 and 4 crossed over to receive ustekinumab (either 45 mg or 90 mg) at Weeks 12 and 16.

In both trials, subjects in all treatment groups had a median baseline PASI score ranging from approximately 17 to 18. Baseline PGA score was marked or severe in 44% of subjects in Ps STUDY 1 and 40% of subjects in Ps STUDY 2. Approximately two-thirds of all subjects had received prior phototherapy, 69% had received either prior conventional systemic or biologic therapy for the treatment of psoriasis, with 56% receiving prior conventional systemic therapy and 43% receiving prior biologic therapy. A total of 28% of subjects had a history of psoriatic arthritis.

In both trials, the endpoints were the proportion of subjects who achieved at least a 75% reduction in PASI score (PASI 75) from baseline to Week 12 and treatment success (cleared or minimal) on the Physician’s Global Assessment (PGA). The PGA is a 6-category scale ranging from 0 (cleared) to 5 (severe) that indicates the physician’s overall assessment of psoriasis focusing on plaque thickness/induration, erythema, and scaling.

Clinical Response

The results of Ps STUDY 1 and Ps STUDY 2 are presented in Table 8 below.

Examination of age, gender, and race subgroups did not identify differences in response to ustekinumab among these subgroups.

In subjects who weighed 100 kg or less, response rates were comparable with both the 45 mg and 90 mg doses; however, in subjects who weighed greater than 100 kg, higher response rates were seen with 90 mg dosing compared with 45 mg dosing (Table 9 below).

Subjects in Ps STUDY 1 who were PASI 75 responders at both Weeks 28 and 40 were re-randomized at Week 40 to either continued dosing of ustekinumab (ustekinumab at Week 40) or to withdrawal of therapy (placebo at Week 40). At Week 52, 89% (144/162) of subjects re-randomized to ustekinumab treatment were PASI 75 responders compared with 63% (100/159) of subjects re-randomized to placebo (treatment withdrawal after Week 28 dose). The median time to loss of PASI 75 response among the subjects randomized to treatment withdrawal was 16 weeks.

14.2 Pediatric Plaque Psoriasis

A multicenter, randomized, double blind, placebo-controlled trial (Ps STUDY 3) enrolled 110 pediatric subjects 12 to 17 years of age with a minimum BSA involvement of 10%, a PASI score greater than or equal to 12, and a PGA score greater than or equal to 3, who were candidates for phototherapy or systemic therapy and whose disease was inadequately controlled by topical therapy.

Subjects were randomized to receive placebo (n = 37), the recommended dose of ustekinumab (n = 36), or one-half the recommended dose of ustekinumab (n = 37) by subcutaneous injection at Weeks 0 and 4 followed by dosing every 12 weeks (q12w). The recommended dose of ustekinumab was 0.75 mg/kg for subjects weighing less than 60 kg, 45 mg for subjects weighing 60 kg to 100 kg, and 90 mg for subjects weighing greater than 100 kg. At Week 12, subjects who received placebo were crossed over to receive ustekinumab at the recommended dose or one-half the recommended dose.

Of the pediatric subjects, approximately 63% had prior exposure to phototherapy or conventional systemic therapy and approximately 11% had prior exposure to biologics.

The endpoints were the proportion of subjects who achieved a PGA score of cleared (0) or minimal (1), PASI 75, and PASI 90 at Week 12. Subjects were followed for up to 60 weeks following first administration of trial agent.

Clinical Response

The efficacy results at Week 12 for Ps STUDY 3 are presented in Table 10.

14.3 Psoriatic Arthritis

The safety and efficacy of ustekinumab was assessed in 927 subjects (PsA STUDY 1, n=615; PsA STUDY 2, n=312), in two randomized, double-blind, placebo-controlled trials in adult subjects 18 years of age and older with active PsA (≥5 swollen joints and ≥5 tender joints) despite nonsteroidal anti-inflammatory (NSAID) or disease modifying antirheumatic (DMARD) therapy. Subjects in these trials had a diagnosis of PsA for at least 6 months. Subjects with each subtype of PsA were enrolled, including polyarticular arthritis with the absence of rheumatoid nodules (39%), spondylitis with peripheral arthritis (28%), asymmetric peripheral arthritis (21%), distal interphalangeal involvement (12%) and arthritis mutilans (0.5%). Over 70% and 40% of the patients, respectively, had enthesitis and dactylitis at baseline.

Subjects were randomized to receive treatment with ustekinumab 45 mg, 90 mg, or placebo subcutaneously at Weeks 0 and 4 followed by every 12 weeks (q12w) dosing. Approximately 50% of subjects continued on stable doses of MTX (≤25 mg/week). The primary endpoint was the percentage of subjects achieving ACR 20 response at Week 24.

In PsA STUDY 1 and PsA STUDY 2, 80% and 86% of the subjects, respectively, had been previously treated with DMARDs. In PsA STUDY 1, previous treatment with anti-tumor necrosis factor (TNF)-α agent was not allowed. In PsA STUDY 2, 58% (n=180) of the subjects had been previously treated with TNF blocker, of whom over 70% had discontinued their TNF blocker treatment for lack of efficacy or intolerance at any time.

Clinical Response

In both trials, a greater proportion of subjects achieved ACR 20, ACR 50 and PASI 75 response in the ustekinumab 45 mg and 90 mg groups compared to placebo at Week 24 (see Table 11). ACR 70 responses were also higher in the ustekinumab 45 mg and 90 mg groups, although the difference was only numerical (p=NS) in STUDY 2. Responses were consistent in subjects treated with ustekinumab alone or in combination with methotrexate. Responses were similar in subjects regardless of prior TNFα exposure.

The percent of subjects achieving ACR 20 responses by visit is shown in Figure 1.

The results of the components of the ACR response criteria are shown in Table 12.

An improvement in enthesitis and dactylitis scores was observed in each ustekinumab group compared with placebo at Week 24.

Physical Function

Ustekinumab-treated subjects showed improvement in physical function compared to subjects treated with placebo as assessed by HAQ-DI at Week 24. In both trials, the proportion of HAQ- DI responders (≥0.3 improvement in HAQ-DI score) was greater in the ustekinumab 45 mg and 90 mg groups compared to placebo at Week 24.

14.4 Crohn’s Disease

Ustekinumab was evaluated in three randomized, double-blind, placebo-controlled clinical trials in adult subjects with moderately to severely active Crohn’s disease (Crohn’s Disease Activity Index [CDAI] score of 220 to 450). There were two 8-week intravenous induction trials (CD-1 and CD-2) followed by a 44-week subcutaneous randomized withdrawal maintenance trial (CD-3) representing 52 weeks of therapy. Subjects in CD-1 had failed or were intolerant to treatment with one or more TNF blockers, while subjects in CD-2 had failed or were intolerant to treatment with immunomodulators or corticosteroids, but never failed treatment with a TNF blocker.

Trials CD-1 and CD-2

In trials CD-1 and CD-2, 1409 subjects were randomized, of whom 1368 (CD-1, n=741; CD-2, n=627) were included in the final efficacy analysis. Induction of clinical response (defined as a reduction in CDAI score of greater than or equal to 100 points or CDAI score of less than 150) at Week 6 and clinical remission (defined as a CDAI score of less than 150) at Week 8 were evaluated. In both trials, subjects were randomized to receive a single intravenous administration of ustekinumab at either approximately 6 mg/kg, placebo (see Table 4), or 130 mg (a lower dose than recommended).

In trial CD-1, subjects had failed or were intolerant to prior treatment with a TNF blocker: 29% subjects had an inadequate initial response (primary non-responders), 69% responded but subsequently lost response (secondary non-responders) and 36% were intolerant to a TNF blocker. Of these subjects, 48% failed or were intolerant to one TNF blocker and 52% had failed 2 or 3 prior TNF blockers. At baseline and throughout the trial, approximately 46% of the subjects were receiving corticosteroids and 31% of the subjects were receiving immunomodulators (AZA, 6-MP, MTX). The median baseline CDAI score was 319 in the ustekinumab approximately 6 mg/kg group and 313 in the placebo group.

In trial CD-2, subjects had failed or were intolerant to prior treatment with corticosteroids (81% of subjects), at least one immunomodulator (6-MP, AZA, MTX; 68% of subjects), or both (49% of subjects). Additionally, 69% never received a TNF blocker and 31% previously received but had not failed a TNF blocker. At baseline, and throughout the trial, approximately 39% of the subjects were receiving corticosteroids and 35% of the subjects were receiving immunomodulators (AZA, 6-MP, MTX). The median baseline CDAI score was 286 in the ustekinumab and 290 in the placebo group.

In these induction trials, a greater proportion of subjects treated with ustekinumab (at the recommended dose of approximately 6 mg/kg dose) achieved clinical response at Week 6 and clinical remission at Week 8 compared to placebo (see Table 13 for clinical response and remission rates). Clinical response and remission were significant as early as Week 3 in ustekinumab-treated subjects and continued to improve through Week 8.

Trial CD-3

The maintenance trial (CD-3) evaluated 388 subjects who achieved clinical response (≥100 point reduction in CDAI score) at Week 8 with either induction dose of ustekinumab in trials CD-1 or CD-2. Subjects were randomized to receive a subcutaneous maintenance regimen of either 90 mg ustekinumab every 8 weeks or placebo for 44 weeks (see Table 14).

At Week 44, 47% of subjects who received ustekinumab were corticosteroid-free and in clinical remission, compared to 30% of subjects in the placebo group.

At Week 0 of trial CD-3, 34/56 (61%) ustekinumab-treated subjects who previously failed or were intolerant to TNF blocker therapies were in clinical remission and 23/56 (41%) of these subjects were in clinical remission at Week 44. In the placebo arm, 27/61 (44%) subjects were in clinical remission at Week 0 while 16/61 (26%) of these subjects were in remission at Week 44.

At Week 0 of trial CD-3, 46/72 (64%) ustekinumab-treated subjects who had previously failed immunomodulator therapy or corticosteroids (but not TNF blockers) were in clinical remission and 45/72 (63%) of these subjects were in clinical remission at Week 44. In the placebo arm, 50/70 (71%) of these subjects were in clinical remission at Week 0 while 31/70 (44%) were in remission at Week 44. In the subset of these subjects who were also naïve to TNF blockers, 34/52 (65%) of ustekinumab-treated subjects were in clinical remission at Week 44 as compared to 25/51 (49%) in the placebo arm.

Subjects who were not in clinical response 8 weeks after ustekinumab induction were not included in the primary efficacy analyses for trial CD-3; however, these subjects were eligible to receive a 90 mg subcutaneous injection of ustekinumab upon entry into trial CD-3. Of these subjects, 102/219 (47%) achieved clinical response eight weeks later and were followed for the duration of the trial.

14.5 Ulcerative Colitis

Ustekinumab was evaluated in two randomized, double-blind, placebo-controlled clinical trials [UC-1 and UC-2 (NCT02407236)] in adult subjects with moderately to severely active ulcerative colitis who had an inadequate response to or failed to tolerate a biologic (i.e., TNF blocker and/or vedolizumab), corticosteroids, and/or 6-MP or AZA therapy. The 8-week intravenous induction trial (UC-1) was followed by the 44-week subcutaneous randomized withdrawal maintenance trial (UC-2) for a total of 52 weeks of therapy.

Disease assessment was based on the Mayo score, which ranged from 0 to 12 and has four subscores that were each scored from 0 (normal) to 3 (most severe): stool frequency, rectal bleeding, findings on centrally-reviewed endoscopy, and physician global assessment. Moderately to severely active ulcerative colitis was defined at baseline (Week 0) as Mayo score of 6 to 12, including a Mayo endoscopy subscore ≥2. An endoscopy score of 2 was defined by marked erythema, absent vascular pattern, friability, erosions; and a score of 3 was defined by spontaneous bleeding, ulceration. At baseline, subjects had a median Mayo score of 9, with 84% of subjects having moderate disease (Mayo score 6-10) and 15% having severe disease (Mayo score 11-12).

Subjects in these trials may have received other concomitant therapies including aminosalicylates, immunomodulatory agents (AZA, 6-MP, or MTX), and oral corticosteroids (prednisone).

Trial UC-1

In UC-1, 961 subjects were randomized at Week 0 to a single intravenous administration of ustekinumab of approximately 6 mg/kg, 130 mg (a lower dose than recommended), or placebo. Subjects enrolled in UC-1 had to have failed therapy with corticosteroids, immunomodulators or at least one biologic. A total of 51% had failed at least one biologic and 17% had failed both a TNF blocker and an integrin receptor blocker. Of the total population, 46% had failed corticosteroids or immunomodulators but were biologic-naïve and an additional 3% had previously received but had not failed a biologic. At induction baseline and throughout the trial, approximately 52% subjects were receiving oral corticosteroids, 28% subjects were receiving immunomodulators (AZA, 6-MP, or MTX) and 69% subjects were receiving aminosalicylates.

The primary endpoint was clinical remission at Week 8. Clinical remission with a definition of: Mayo stool frequency subscore of 0 or 1, Mayo rectal bleeding subscore of 0 (no rectal bleeding), and Mayo endoscopy subscore of 0 or 1 (Mayo endoscopy subscore of 0 defined as normal or inactive disease and Mayo subscore of 1 defined as presence of erythema, decreased vascular pattern and no friability) is provided in Table 15.

The secondary endpoints were clinical response, endoscopic improvement, and histologic- endoscopic mucosal improvement. Clinical response with a definition of (≥ 2 points and ≥ 30% decrease in modified Mayo score, defined as 3-component Mayo score without the Physician’s Global Assessment, with either a decrease from baseline in the rectal bleeding subscore ≥1 or a rectal bleeding subscore of 0 or 1), endoscopic improvement with a definition of Mayo endoscopy subscore of 0 or 1, and histologic-endoscopic mucosal improvement with a definition of combined endoscopic improvement and histologic improvement of the colon tissue [neutrophil infiltration in <5% of crypts, no crypt destruction, and no erosions, ulcerations, or granulation tissue] are provided in Table 15.

In UC-1, a significantly greater proportion of subjects treated with ustekinumab (at the recommended dose of approximately 6 mg/kg dose) were in clinical remission and response and achieved endoscopic improvement and histologic-endoscopic mucosal improvement compared to placebo (see Table 15).

Table 15: Proportion of Subjects Meeting Efficacy Endpoints at Week 8 in UC-1

† Infusion dose of ustekinumab using the weight-based dosage regimen specified in Table 4.

⸸ An additional 7 subjects on placebo and 9 subjects on ustekinumab (6 mg/kg) had been exposed to, but had not failed, biologics.

* * Clinical remission was defined as Mayo stool frequency subscore of 0 or 1, Mayo rectal bleeding subscore of 0, and Mayo endoscopy subscore of 0 or 1 (modified so that 1 does not include friability).

§ Endoscopic improvement was defined as Mayo endoscopy subscore of 0 or 1 (modified so that 1 does not include friability).

† † Clinical response was defined as a decrease from baseline in the modified Mayo score by ≥30% and ≥2 points, with either a decrease from baseline in the rectal bleeding subscore ≥1 or a rectal bleeding subscore of 0 or 1.

‡ ‡ Histologic-endoscopic mucosal improvement was defined as combined endoscopic improvement (Mayo endoscopy subscore of 0 or 1) and histologic improvement of the colon tissue (neutrophil infiltration in <5% of crypts, no crypt destruction, and no erosions, ulcerations, or granulation tissue).

a Adjusted treatment difference (97.5% CI)

b p < 0.001

The relationship of histologic-endoscopic mucosal improvement, as defined in UC-1, at Week 8 to disease progression and long-term outcomes was not evaluated during UC-1.

Rectal Bleeding and Stool Frequency Subscores

Decreases in rectal bleeding and stool frequency subscores were observed as early as Week 2 in ustekinumab-treated subjects.

Trial UC-2

The maintenance trial (UC-2) evaluated 523 subjects who achieved clinical response 8 weeks following the intravenous administration of either induction dose of ustekinumab in UC-1. These subjects were randomized to receive a subcutaneous maintenance regimen of either 90 mg ustekinumab every 8 weeks, or every 12 weeks (a lower dose than recommended), or placebo for 44 weeks.

The primary endpoint was the proportion of subjects in clinical remission at Week 44. The secondary endpoints included the proportion of subjects maintaining clinical response at Week 44, the proportion of subjects with endoscopic improvement at Week 44, the proportion of subjects with corticosteroid-free clinical remission at Week 44, and the proportion of subjects maintaining clinical remission at Week 44 among subjects who achieved clinical remission 8 weeks after induction.

Results of the primary and secondary endpoints at Week 44 in subjects treated with ustekinumab at the recommended dosage (90 mg every 8 weeks) compared to the placebo are shown in Table 16.

Table 16: Efficacy Endpoints of Maintenance at Week 44 in UC-2 (52 Weeks from Initiation of the Induction Dose)

⸸ An additional 3 subjects on placebo and 6 subjects on ustekinumab had been exposed to, but had not failed, biologics.

* The placebo group consisted of subjects who were in response to ustekinumab and were randomized to receive placebo at the start of maintenance therapy.

** Clinical remission was defined as Mayo stool frequency subscore of 0 or 1, Mayo rectal bleeding subscore of 0, and Mayo endoscopy subscore of 0 or 1 (modified so that 1 does not include friability).

† Clinical response was defined as a decrease from baseline in the modified Mayo score by ≥30% and ≥2 points, with either a decrease from baseline in the rectal bleeding subscore ≥1 or a rectal bleeding subscore of 0 or 1.

§ Endoscopic improvement was defined as Mayo endoscopy subscore of 0 or 1 (modified so that 1 does not include friability).

‡ Corticosteroid-free clinical remission was defined as subjects in clinical remission and not receiving corticosteroids at Week 44.

a p =<0.001

b p=0.004

Other Endpoints

Week 16 Responders to Ustekinumab Induction

Subjects who were not in clinical response 8 weeks after induction with ustekinumab in UC-1 were not included in the primary efficacy analyses for trial UC-2; however, these subjects were eligible to receive a 90 mg subcutaneous injection of ustekinumab at Week 8. Of these subjects, 55/101 (54%) achieved clinical response eight weeks later (Week 16) and received ustekinumab 90 mg subcutaneously every 8 weeks during the UC-2 trial. At Week 44, there were 97/157 (62%) subjects who maintained clinical response and there were 51/157 (32%) who achieved clinical remission.

Histologic-Endoscopic Mucosal Improvement at Week 44

The proportion of subjects achieving histologic-endoscopic mucosal improvement during maintenance treatment in UC-2 was 75/172 (44%) among subjects on ustekinumab and 40/172 (23%) in subjects on placebo at Week 44. The relationship of histologic-endoscopic mucosal improvement, as defined in UC-2, at Week 44 to progression of disease or long-term outcomes was not evaluated in UC-2.

Endoscopic Normalization

Normalization of endoscopic appearance of the mucosa was defined as a Mayo endoscopic subscore of 0. At Week 8 in UC-1, endoscopic normalization was achieved in 25/322 (8%) of subjects treated with ustekinumab and 12/319 (4%) of subjects in the placebo group. At Week 44 of UC-2, endoscopic normalization was achieved in 51/176 (29%) of subjects treated with ustekinumab and in 32/175 (18%) of subjects in placebo group.

15 REFERENCES

^1 Surveillance, Epidemiology, and End Results (SEER) Program (www.seer.cancer.gov) SEER*Stat Database: Incidence - SEER 6.6.2 Regs Research Data, Nov 2009 Sub (1973-2007) - Linked To County Attributes - Total U.S., 1969-2007 Counties, National Cancer Institute, DCCPS, Surveillance Research Program, Surveillance Systems Branch, released April 2010, based on the November 2009 submission.

16 HOW SUPPLIED/STORAGE AND HANDLING

STARJEMZA™ (ustekinumab-hmny) injection is a sterile, preservative-free, clear, colorless to light yellow solution. It is supplied as individually packaged, single-dose prefilled syringes or single-dose vials.

For Subcutaneous Use

Prefilled Syringes

- 45 mg/0.5 mL (NDC 0143-9168-01)

- 90 mg/mL (NDC 0143-9170-01)

Each prefilled syringe is equipped with a 27-gauge fixed 1/2 inch needle, a needle safety guard, and a needle cover that contains dry natural rubber.

Single-dose Vial

- 45 mg/0.5 mL (NDC 0143-9169-01)

For Intravenous Infusion

Single-dose Vial

- 130 mg/26 mL (5 mg/mL) (NDC 0143-9171-01)

Storage and Stability

Store STARJEMZA vials and prefilled syringes refrigerated between 2ºC to 8ºC (36ºF to 46ºF). Keep the product in the original carton to protect from light until the time of use. Do not freeze. Do not shake.

If needed, individual prefilled syringe may be stored at room temperature up to 30°C (86°F) for a maximum single period of up to 30 days in the original carton to protect from light. Record the date when the prefilled syringe is first removed from the refrigerator on the carton in the space provided. Discard the prefilled syringe if not used within 30 days at room temperature storage. An individual 45 mg vial may be stored at room temperature, up to 25℃ (77°F), out of the original carton for up to 8 hours. After filling STARJEMZA into the syringe with attached needle, the filled syringe with needle can be stored at up to 25℃ (77°F) for up to 4 hours before injection. Once the prefilled syringe or the 45 mg vial has been stored at room temperature, do not return it to the refrigerator. Do not use STARJEMZA after the expiration date on the carton or on the prefilled syringe or on the 45 mg vial.

17 PATIENT COUNSELING INFORMATION

Advise the patient and/or caregiver to read the FDA-approved patient labeling (Medication Guide and Instructions for Use).

Infections

Inform patients that STARJEMZA may lower the ability of their immune system to fight infections and to contact their healthcare provider immediately if they develop any signs or symptoms of infection [see Warnings and Precautions (5.1)].

Malignancies

Inform patients of the risk of developing malignancies while receiving STARJEMZA [see Warnings and Precautions (5.4)].

Hypersensitivity Reactions

- Advise patients to seek immediate medical attention if they experience any signs or symptoms of serious hypersensitivity reactions and discontinue STARJEMZA [see Warnings and Precautions (5.5)].
- Inform patients the needle cover on the prefilled syringe contains dry natural rubber (a derivative of latex), which may cause allergic reactions in individuals sensitive to latex [see Dosage and Administration (2.4)].

Posterior Reversible Encephalopathy Syndrome (PRES)

Inform patients to immediately contact their healthcare provider if they experience signs and symptoms of PRES (which may include headache, seizures, confusion, or visual disturbances) [see Warnings and Precautions (5.6)].

Immunizations

Inform patients that STARJEMZA can interfere with the usual response to immunizations and that they should avoid live vaccines [see Warnings and Precautions (5.7)].

Administration

Instruct patients to follow sharps disposal recommendations, as described in the Instructions for Use.

Manufactured by:
Bio-Thera Solutions, Ltd.
155 Yaotianhe Street, Huangpu District,
Guangzhou, Guangdong, China 511356
Distributed by:
Hikma Pharmaceuticals USA Inc.
Berkeley Heights, NJ 07922
U.S. License Number 2218
STARJEMZA is a trademark of Hikma Pharmaceuticals USA Inc.
STELARA is a trademark of Johnson & Johnson.
© 2025 Hikma Pharmaceuticals USA Inc. All rights reserved.

MEDICATION GUIDE

STARJEMZA™ (star jem' zah)

(ustekinumab-hmny)

injection, for subcutaneous or intravenous use

What is the most important information I should know about STARJEMZA?

STARJEMZA is a medicine that affects your immune system. STARJEMZA can increase your risk of having serious side effects, including:

Serious infections. STARJEMZA may lower the ability of your immune system to fight infections and may increase your risk of infections. Some people have serious infections while taking ustekinumab products, including tuberculosis (TB), and infections caused by bacteria, fungi, or viruses. Some people have to be hospitalized for treatment of their infection.

- Your doctor should check you for TB before starting STARJEMZA.
- If your doctor feels that you are at risk for TB, you may be treated with medicine for TB before you begin treatment with STARJEMZA and during treatment with STARJEMZA.
- Your doctor should watch you closely for signs and symptoms of TB while you are being treated with STARJEMZA. You should not start taking STARJEMZA if you have any kind of infection unless your doctor says it is okay.

Before starting STARJEMZA, tell your doctor if you:

- think you have an infection or have symptoms of an infection such as:
  - fever, sweat, or chills o warm, red, or painful skin or sores on your body
  - muscle aches o diarrhea or stomach pain
  - cough o burning when you urinate or urinate more often than normal
  - shortness of breath o feel very tired
  - blood in phlegm
  - weight loss
- are being treated for an infection or have any open cuts.
- get a lot of infections or have infections that keep coming back.
- have TB, or have been in close contact with someone with TB.

After starting STARJEMZA, call your doctor right away if you have any symptoms of an infection (see above). These may be signs of infections such as chest infections, or skin infections or shingles that could have serious complications. STARJEMZA can make you more likely to get infections or make an infection that you have worse. People who have a genetic problem where the body does not make any of the proteins interleukin 12 (IL-12) and interleukin 23 (IL-23) are at a higher risk for certain serious infections. These infections can spread throughout the body and cause death. People who take STARJEMZA may also be more likely to get these infections.

Cancers. STARJEMZA may decrease the activity of your immune system and increase your risk for certain types of cancers. Tell your doctor if you have ever had any type of cancer. Some people who are receiving ustekinumab products and have risk factors for skin cancer have developed certain types of skin cancers. During your treatment with STARJEMZA, tell your doctor if you develop any new skin growths.

Posterior Reversible Encephalopathy Syndrome (PRES). PRES is a rare condition that affects the brain and can cause death. The cause of PRES is not known. If PRES is found early and treated, most people recover. Tell your doctor right away if you have any new or worsening medical problems including:

o headache o confusion

o seizures o vision problems

What is STARJEMZA?

STARJEMZA is a prescription medicine used to treat:

- adults and children 6 years and older with moderate or severe psoriasis who may benefit from taking injections or pills (systemic therapy) or phototherapy (treatment using ultraviolet light alone or with pills).
- adults and children 6 years and older with active psoriatic arthritis.
- adults 18 years and older with moderately to severely active Crohn’s disease.
- adults 18 years and older with moderately to severely active ulcerative colitis.

It is not known if STARJEMZA is safe and effective in children less than 6 years of age.

Do not take STARJEMZA if you are allergic to ustekinumab products or any of the ingredients in STARJEMZA. See the end of this Medication Guide for a complete list of ingredients in STARJEMZA.

Before you receive STARJEMZA, tell your doctor about all of your medical conditions, including if you:

- have any of the conditions or symptoms listed in the section “What is the most important information I should know about STARJEMZA?”
- ever had an allergic reaction to ustekinumab products. Ask your doctor if you are not sure.
- are allergic to latex. The needle cover on the prefilled syringe contains latex.
- have recently received or are scheduled to receive an immunization (vaccine). People who take STARJEMZA should not receive live vaccines. Tell your doctor if anyone in your house needs a live vaccine. The viruses used in some types of live vaccines can spread to people with a weakened immune system, and can cause serious problems. You should not receive the BCG vaccine during the one year before receiving STARJEMZA or one year after you stop receiving STARJEMZA.
- have any new or changing lesions within psoriasis areas or on normal skin.
- are receiving or have received allergy shots, especially for serious allergic reactions. Allergy shots may not work as well for you during treatment with STARJEMZA. STARJEMZA may also increase your risk of having an allergic reaction to an allergy shot.
- receive or have received phototherapy for your psoriasis.
- are pregnant or plan to become pregnant. It is not known if STARJEMZA can harm your unborn baby. You and your doctor should decide if you will receive STARJEMZA. See “What should I avoid while using STARJEMZA?”
- received STARJEMZA while you were pregnant. It is important that you tell your baby’s healthcare provider before any vaccinations are given to your baby.
- are breastfeeding or plan to breastfeed. STARJEMZA can pass into your breast milk.
- Talk to your doctor about the best way to feed your baby if you receive STARJEMZA.

Tell your doctor about all the medicines you take, including prescription and over-the-counter medicines, vitamins, and herbal supplements.

Know the medicines you take. Keep a list of them to show your doctor and pharmacist when you get a new medicine.

How should I use STARJEMZA?

- Use STARJEMZA exactly as your doctor tells you to.
- The needle cover on the STARJEMZA prefilled syringe contains latex. Do not handle the needle cover if you are sensitive to latex.
- Adults with Crohn’s disease and ulcerative colitis will receive the first dose of STARJEMZA through a vein in the arm (intravenous infusion) in a healthcare facility by a healthcare provider. It takes at least 1 hour to receive the full dose of medicine. You will then receive STARJEMZA as an injection under the skin (subcutaneous injection) 8 weeks after the first dose of STARJEMZA, as described below.
- Adults with psoriasis or psoriatic arthritis, and children 6 years and older with psoriasis or psoriatic arthritis will receive STARJEMZA as an injection under the skin (subcutaneous injection) as described below.
- Injecting STARJEMZA under your skin
  - STARJEMZA is intended for use under the guidance and supervision of your doctor. In children 6 years and older, it is recommended that STARJEMZA be administered by a healthcare provider. If your doctor decides that you or a caregiver may give your injections of STARJEMZA at home, you should receive training on the right way to prepare and inject STARJEMZA. Your doctor will determine the right dose of STARJEMZA for you, the amount for each injection, and how often you should receive it. Do not try to inject STARJEMZA yourself until you or your caregiver have been shown how to inject STARJEMZA by your doctor or nurse.
  - Inject STARJEMZA under the skin (subcutaneous injection) in your upper arms, buttocks, upper legs (thighs) or stomach area (abdomen).
  - Do not give an injection in an area of the skin that is tender, bruised, red or hard.
  - Use a different injection site each time you use STARJEMZA.
  - If you inject more STARJEMZA than prescribed, call your doctor right away.
  - Be sure to keep all of your scheduled follow-up appointments.

Read the detailed Instructions for Use at the end of this Medication Guide for instructions about how to prepare and inject a dose of STARJEMZA, and how to properly throw away (dispose of) used needles and syringes. The syringe, needle and vial must never be re-used. After the rubber stopper is punctured, STARJEMZA can become contaminated by harmful bacteria which could cause an infection if re-used. Therefore, throw away any unused portion of STARJEMZA.

What should I avoid while using STARJEMZA?

You should not receive a live vaccine while taking STARJEMZA. See “Before you receive STARJEMZA, tell your doctor about all of your medical conditions, including if you:”

What are the possible side effects of STARJEMZA?

STARJEMZA may cause serious side effects, including:

- See “What is the most important information I should know about STARJEMZA?”
- Serious allergic reactions. Serious allergic reactions can occur with STARJEMZA. Stop using STARJEMZA and get medical help right away if you have any of the following symptoms of a serious allergic reaction:
  o feeling faint o chest tightness
  o swelling of your face, eyelids, tongue or throat o skin rash
- Lung inflammation. Cases of lung inflammation have happened in some people who receive ustekinumab products, and may be serious. These lung problems may need to be treated in a hospital. Tell your doctor right away if you develop shortness of breath or a cough that doesn’t go away during treatment with STARJEMZA.

Common side effects of STARJEMZA include:

- nasal congestion, sore throat, and runny nose
- redness at the injection site
- upper respiratory infections
- vaginal yeast infections
- fever
- urinary tract infections
- headache
- sinus infection
- tiredness
- bronchitis
- itching
- diarrhea
- nausea and vomiting
- stomach pain

These are not all of the possible side effects of STARJEMZA. Call your doctor for medical advice about side effects. You may report side effects to FDA at 1-800-FDA-1088.

You may also report side effects to Hikma Pharmaceuticals USA Inc. at 1-877-845-0689.

How should I store STARJEMZA?

- Store STARJEMZA vials and prefilled syringes in a refrigerator between 2°C to 8°C (36°F to 46°F).
- Store STARJEMZA in the original carton to protect it from light until time to use it.
- Do not freeze STARJEMZA.
- Do not shake STARJEMZA.

If needed, individual STARJEMZA prefilled syringe may also be stored at room temperature up to 86°F (30ºC) for a maximum single period of up to 30 days in the original carton to protect from light. Record the date when the prefilled syringe is first removed from the refrigerator on the carton in the space provided. Discard the prefilled syringe if not used within 30 days at room temperature storage.

An individual 45 mg vial may be stored at room temperature, up to 25°C (77°F) out of the original carton for up to 8 hours. After filling STARJEMZA into the syringe with attached needle, the filled syringe with needle can be stored at up to 25°C (77°F) for up to 4 hours before injection. Once the prefilled syringe or the 45 mg vial has been stored at room temperature, it should not be returned to the refrigerator. Do not use STARJEMZA after the expiration date on the carton or on the prefilled syringe or on the 45 mg vial.

Keep STARJEMZA and all medicines out of the reach of children.

General information about the safe and effective use of STARJEMZA.
Medicines are sometimes prescribed for purposes other than those listed in a Medication Guide. Do not use STARJEMZA for a condition for which it was not prescribed. Do not give STARJEMZA to other people, even if they have the same symptoms that you have. It may harm them. You can ask your doctor or pharmacist for information about STARJEMZA that was written for health professionals.

What are the ingredients in STARJEMZA?

Active ingredient: ustekinumab-hmny

Inactive ingredients: Single-dose prefilled syringe for subcutaneous use contains histidine, L-histidine hydrochloride monohydrate, polysorbate 80, and sucrose. Single-dose vial for subcutaneous use contains histidine, L-histidine hydrochloride monohydrate, polysorbate 80 and sucrose. Single-dose vial for intravenous infusion contains edetate disodium, histidine, L-histidine hydrochloride monohydrate, methionine, polysorbate 80, and sucrose.

Manufactured by: Bio-Thera Solutions, Ltd., 155 Yaotianhe Street, Huangpu District, Guangzhou, Guangdong, China 511356

Distributed by: Hikma Pharmaceuticals USA Inc., Berkeley Heights, NJ 07922

U.S. License No. 2218

© 2025 Hikma Pharmaceuticals USA Inc. All rights reserved.

For more information, go to www.hikma.com or call 1-877-845-0689.

This Medication Guide has been approved by the U.S. Food and Drug Administration. Revised: 05/2025

INSTRUCTIONS FOR USE

STARJEMZA™ (star jem' zah)

(ustekinumab-hmny)

injection, for subcutaneous use

Instructions for injecting STARJEMZA from a vial.

Read this Instructions for Use before you start using STARJEMZA. Your doctor or nurse should show you how to prepare, measure your dose, and give your injection of STARJEMZA the right way.

If you cannot give yourself the injection:

- ask your doctor or nurse to help you, or
- ask someone who has been trained by a doctor or nurse to give your injections.

Do not try to inject STARJEMZA yourself until you have been shown how to inject STARJEMZA by your doctor, nurse or health professional.

Important information:

- Before you start, check the carton to make sure that it is the right dose. You will have either 45 mg or 90 mg as prescribed by your doctor.
  - If your dose is 45 mg or less you will receive one 45 mg vial.
  - If your dose is 90 mg, you will receive two 45 mg vials and you will need to give yourself two injections, one right after the other.
- Children 12 years of age and older weighing less than 132 pounds require a dose lower than 45 mg.
- Store STARJEMZA vials in a refrigerator between 2°C to 8°C (36°F to 46°F).
- Store STARJEMZA in the original carton to protect it from light until time to use it.
- Check the expiration date on the vial and carton. If the expiration date has passed, do not use it. If the expiration date has passed, call your doctor or pharmacist, or call Hikma Pharmaceuticals USA Inc. at 1-877-845-0689 for help.
- Check the vial for any particles or discoloration. Your vial should look clear and colorless to light yellow.
- Do not use if it is frozen, discolored, cloudy or has particles. Get a new vial.
- An individual 45 mg vial may be stored at room temperature, up to 25°C (77°F), out of the original carton for up to 8 hours. After filling STARJEMZA into the syringe with attached needle, the filled syringe with needle can be stored at up to 25°C (77°F) for up to 4 hours before injection. Once the 45 mg vial has been stored at room temperature, do not return it to the refrigerator. Do not use STARJEMZA after the expiration date on the carton or on the 45 mg vial.
- Do not shake the vial at any time. Shaking your vial may damage your STARJEMZA medicine. If your vial has been shaken, do not use it. Get a new vial.
- Do not use a STARJEMZA vial more than one time, even if there is medicine left in the vial. After the rubber stopper is punctured, STARJEMZA can become contaminated by harmful bacteria which could cause an infection if re-used. Therefore, throw away any unused STARJEMZA after you give your injection.
- Safely throw away (dispose of) STARJEMZA vials after use.
- Do not re-use syringes or needles. See “Step 6: Dispose of needles and syringes.”
- To avoid needle-stick injuries, do not recap needles.

Gather the supplies you will need to prepare STARJEMZA and to give your injection. (See Figure A)

You will need:

- a syringe with the needle attached, you will need a prescription from your healthcare provider to get syringes with the needles attached from your pharmacy
- antiseptic wipes
- cotton balls or gauze pads
- adhesive bandage
- your prescribed dose of STARJEMZA
- FDA-cleared sharps disposal container. See “Step 6: Dispose of needles and syringes.”

Step 1: Prepare the injection

- Choose a well-lit, clean, flat work surface.
- Wash your hands well with soap and warm water.

Step 2: Prepare your injection site

- Choose an injection site around your stomach area (abdomen), buttocks, and upper legs (thighs).
- If a caregiver is giving you the injection, the outer area of the upper arms may also be used. (See Figure B)
- Use a different injection site for each injection. Do not give an injection in an area of the skin that is tender, bruised, red or hard.
- Clean the skin with an antiseptic wipe where you plan to give your injection.
- Do not touch this area again before giving the injection. Let your skin dry before injecting.
- Do not fan or blow on the clean area.

Step 3: Prepare the vial

- Remove the cap from the top of the vial. Throw away the cap but do not remove the rubber stopper. (See Figure C)

- Clean the rubber stopper with an antiseptic wipe. (See Figure D)

- Do not touch the rubber stopper after you clean it.
- Put the vial on a flat surface.

Step 4: Prepare the needle

- Pick up the syringe with the needle attached.
- Remove the cap that covers the needle. (See Figure E)
- Throw the needle cap away. Do not touch the needle or allow the needle to touch anything.

- Carefully pull back on the plunger to the line that matches the dose prescribed by your doctor.
- Hold the vial between your thumb and index (pointer) finger.
- Use your other hand to push the syringe needle through the center of the rubber stopper. (See Figure F)

- Push down on the plunger until all of the air has gone from the syringe into the vial.
- Turn the vial and the syringe upside down. (See Figure G)
- Hold the STARJEMZA vial with one hand.
- It is important that the needle is always in the liquid in order to prevent air bubbles forming in the syringe.
- Pull back on the syringe plunger with your other hand.
- Fill the syringe until the black tip of the plunger lines up with the mark that matches your prescribed dose.

- Do not remove the needle from the vial. Hold the syringe with the needle pointing up to see if it has any air bubbles inside.
- If there are air bubbles, gently tap the side of the syringe until the air bubbles rise to the top. (See Figure H)
- Slowly press the plunger up until all of the air bubbles are out of the syringe (but none of the liquid is out).
- Remove the syringe from the vial. Do not lay the syringe down or allow the needle to touch anything.

Step 5: Inject STARJEMZA

- Hold the barrel of the syringe in one hand, between the thumb and index fingers.
- Do not pull back on the plunger at any time.
- Use the other hand to gently pinch the cleaned area of skin. Hold firmly.
- Use a quick, dart-like motion to insert the needle into the pinched skin at about a 45-degree angle. (See Figure I)

- Push the plunger with your thumb as far as it will go to inject all of the liquid. Push it slowly and evenly, keeping the skin gently pinched.
- When the syringe is empty, pull the needle out of your skin and let go of the skin. (See Figure J)

- When the needle is pulled out of your skin, there may be a little bleeding at the injection site. This is normal. You can press a cotton ball or gauze pad to the injection site if needed. Do not rub the injection site. You may cover the injection site with a small adhesive bandage, if necessary.

If your dose is 90 mg, you will receive two 45 mg vials and you will need to give yourself a second injection right after the first. Repeat Steps 1 to 5 using a new syringe. Choose a different site for the second injection.

Step 6: Dispose of the needles and syringes

- Do not re-use a syringe or needle.
- To avoid needle-stick injuries, do not recap a needle.
- Put your needles and syringes in a FDA-cleared sharps disposal container right away after use. Do not throw away (dispose of) loose needles and syringes in your household trash.
- If you do not have a FDA-cleared sharps disposal container, you may use a household container that is:
  - made of heavy-duty plastic
  - can be closed with a tight-fitting, puncture-resistant lid, without sharps being able to come out
  - upright and stable during use
  - leak-resistant,
  - and properly labeled to warn of hazardous waste inside the container.
- When your sharps disposal container is almost full, you will need to follow your community guidelines for the right way to dispose of your sharps disposal container. There may be local or state laws about how to throw away syringes and needles. For more information about safe sharps disposal, and for specific information about sharps disposal in the state that you live in, go to the FDA’s website at: http://www.fda.gov/safesharpsdisposal.
- Do not dispose of your sharps disposal container in your household trash unless your community guidelines permit this. Do not recycle your sharps disposal container.
- Throw away the vial into the container where you put the syringes and needles.
- If you have any questions, talk to your doctor or pharmacist.

Keep STARJEMZA and all medicines out of the reach of children.

Manufactured by:
Bio-Thera Solutions, Ltd.
155 Yaotianhe Street, Huangpu District,
Guangzhou, Guangdong, China 511356
Distributed by:
Hikma Pharmaceuticals USA Inc.
Berkeley Heights, NJ 07922

U.S. License No. 2218

This Instructions for Use has been approved by the U.S. Food and Drug Administration.

Revised: 05/2025

© 2025 Hikma Pharmaceuticals USA Inc. All rights reserved.

INSTRUCTIONS FOR USE

STARJEMZA™ (star jem' zah)

(ustekinumab-hmny)

injection, for subcutaneous use

Instructions for injecting STARJEMZA using a prefilled syringe.

Read this Instructions for Use before you start using STARJEMZA. Your doctor or nurse should show you how to prepare and give your injection of STARJEMZA the right way.

If you cannot give yourself the injection:

- ask your doctor or nurse to help you, or

- ask someone who has been trained by a doctor or nurse to give your injections.

Do not try to inject STARJEMZA yourself until you have been shown how to inject STARJEMZA by your doctor, nurse or health professional.

Important information:

- Before you start, check the carton to make sure that it is the right dose. You will have either 45 mg or 90 mg as prescribed by your doctor.
  - If your dose is 45 mg, you will receive one 45 mg prefilled syringe.
  - If your dose is 90 mg, you will receive either one 90 mg prefilled syringe or two 45 mg prefilled syringes. If you receive two 45 mg prefilled syringes for a 90 mg dose, you will need to give yourself two injections, one right after the other.
- Children 12 years of age and older with psoriasis who weigh 132 pounds or more may use a prefilled syringe.
- Store STARJEMZA prefilled syringes in a refrigerator between 2°C to 8°C (36°F to 46°F).
- Store STARJEMZA in the original carton to protect it from light until time to use it.
- Check the expiration date on the prefilled syringe and carton. If the expiration date has passed or if the prefilled syringe has been kept at room temperature up to 30ºC (86ºF) for longer than a maximum single period of 30 days or if the prefilled syringe has been stored above 30ºC (86ºF), do not use it. If the expiration date has passed or if the prefilled syringe has been stored above 30ºC (86ºF), call your doctor or pharmacist, or call Hikma Pharmaceuticals USA Inc.at 1-877-845-0689 for help.
- Make sure the syringe is not damaged.
- The needle cover on the prefilled syringe contains latex. Do not handle the needle cover on the STARJEMZA prefilled syringe if you are allergic to latex.
- Check your prefilled syringe for any particles or discoloration. Your prefilled syringe should look clear and colorless to light yellow.
- Do not use if it is frozen, discolored, cloudy or has particles. Get a new prefilled syringe.
- Before administration, wait 30 minutes for the syringe to reach room temperature. Let the syringe warm up naturally. Do not heat with hot water, a microwave, or direct sunlight. Using the syringe at room temperature allows for a more comfortable injection.
- Do not shake the prefilled syringe at any time. Shaking your prefilled syringe may damage your STARJEMZA medicine. If your prefilled syringe has been shaken, do not use it. Get a new prefilled syringe.
- To reduce the risk of accidental needle sticks, each prefilled syringe has a needle guard that is automatically activated to cover the needle after you have given your injection. Do not pull back on the plunger at any time.

Gather the supplies you will need to prepare and to give your injection. (See Figure A)

You will need:

- antiseptic wipes

- cotton balls or gauze pads

- adhesive bandage

- your prescribed dose of STARJEMZA (See Figure B)

- FDA-cleared sharps disposal container. See “Step 4: Dispose of the syringe.”

Step 1: Prepare the injection.

- Choose a well-lit, clean, flat work surface.

- Wash your hands well with soap and warm water.

- Hold the prefilled syringe with the covered needle pointing upward.

Step 2: Prepare your injection site

- Choose an injection site around your stomach area (abdomen), buttocks, upper legs (thighs). If a caregiver is giving you the injection, the outer area of the upper arms may also be used. (See Figure C)
- Use a different injection site for each injection. Do not give an injection in an area of the skin that is tender, bruised, red or hard.
- Clean the skin with an antiseptic wipe where you plan to give your injection.
- Do not touch this area again before giving the injection. Let your skin dry before injecting.
- Do not fan or blow on the clean area.

Step 3: Inject STARJEMZA

- Remove the needle cover when you are ready to inject your STARJEMZA.

- Do not touch the plunger while removing the needle cover.

- Hold the body of the prefilled syringe with one hand, and pull the needle cover straight off. (see Figure D)

- Put the needle cover in the trash.

- You may also see a drop of liquid at the end of the needle. This is normal.

- Do not touch the needle or let it touch anything.

- Do not use the prefilled syringe if it is dropped without the needle cover in place. Call your doctor, nurse or health professional for instructions.

- Hold the body of the prefilled syringe in one hand between the thumb and index fingers. (See Figure E)

- Do not pull back on the plunger at any time.

- Use the other hand to gently pinch the cleaned area of skin. Hold firmly.
- Use a quick, dart-like motion to insert the needle into the pinched skin at about a 45-degree angle. (See Figure F)

- Inject all of the liquid by using your thumb to push in the plunger until the plunger head is completely between the needle guard wings.(See Figure G)

- When the plunger is pushed as far as it will go, keep pressure on the plunger head. Take the needle out of the skin and let go of the skin.(See Figure H)

- Slowly take your thumb off the plunger head. This will let the empty syringe move up until the entire needle is covered by the needle guard.(See Figure I)

- When the needle is pulled out of your skin, there may be a little bleeding at the injection site. This is normal. You can press a cotton ball or gauze pad to the injection site if needed. Do not rub the injection site. You may cover the injection site with a small adhesive bandage, if necessary.

If your dose is 90 mg, you will receive either one 90 mg prefilled syringe or two 45 mg prefilled syringes. If you receive two 45 mg prefilled syringes for a 90 mg dose, you will need to give yourself a second injection right after the first. Repeat Steps 1-3 for the second injection using a new syringe. Choose a different site for the second injection.

Step 4: Dispose of the syringe.

- Put the syringe in an FDA-cleared sharps disposal container right away after use. Do not throw away (dispose of) loose syringes in your household trash.

- If you do not have an FDA-cleared sharps disposal container, you may use a household container that is:

- made of heavy-duty plastic.

- can be closed with a tight-fitting, puncture-resistant lid, without sharps being able to come out.

- upright and stable during use,

- leak-resistant,

- and properly labeled to warn of hazardous waste inside the container.

- When your sharps disposal container is almost full, you will need to follow your community guidelines for the right way to dispose of your sharps disposal container. There may be local or state laws about how to throw away syringes and needles. For more information about safe sharps disposal, and for specific information about sharps disposal in the state that you live in, go to the FDA's website at: http://www.fda.gov/safesharpsdisposal.

- Do not dispose of your sharps disposal container in your household trash unless your community guidelines permit this. Do not recycle your sharps disposal container.

- If you have any questions, talk to your doctor or pharmacist.

Keep STARJEMZA and all medicines out of the reach of children.

Manufactured by:

Bio-Thera Solutions, Ltd.

155 Yaotianhe Street, Huangpu District,

Guangzhou, Guangdong, China 511356

Distributed by:

Hikma Pharmaceuticals USA Inc.

Berkeley Heights, NJ 07922

This Instructions for Use has been approved by the U.S. Food and Drug Administration.

Approved: 05/2025

© 2025 Hikma Pharmaceuticals USA Inc. All rights reserved.

PRINCIPAL DISPLAY PANEL

45 mg/0.5 mL - Syringe Label

NDC 0143-9168-01

Rx only

Starjemza

Ustekinumab-hmny

Injection

45 mg/0.5 mL

For subcutaneous use

Single-Dose Prefilled Syringe

Discard unused portion

45 mg/0.5 mL - Syringe Carton Label

NDC 0143-9168-01

Rx only

Starjemza

Ustekinumab-hmny

Injection

45 mg/0.5 mL

For subcutaneous use

Single-Dose Prefilled Syringe

Discard unused portion

NDC 0143-9168-01 45 mg/0.5 mL

PRINCIPAL DISPLAY PANEL

45 mg/0.5 mL - Vial Label

NDC 0143-9169-01

Rx only

Starjemza

Ustekinumab-hmny

Injection

45 mg/0.5 mL

For subcutaneous use

Single-Dose Vial

Discard unused portion

45 mg/0.5 mL - Vial Carton Label

NDC 0143-9169-01

Rx only

Starjemza

Ustekinumab-hmny

Injection

45 mg/0.5 mL

For subcutaneous use

Single-Dose Vial

Discard unused portion

PRINCIPAL DISPLAY PANEL

90 mg/mL - Syringe Label

NDC 0143-9170-01

Rx only

Starjemza

Ustekinumab-hmny

Injection

90 mg/mL

For subcutaneous use

Single-Dose Prefilled Syringe

Discard unused portion

90 mg/mL - Syringe Carton Label

NDC 0143-9170-01

Rx only

Starjemza

Ustekinumab-hmny

Injection

90 mg/mL

For subcutaneous use

Single-dose prefilled syringe

Discard unused portion

PRINCIPAL DISPLAY PANEL

130 mg/26 mL - Vial Label

NDC 0143-9171-01

Rx only

Starjemza

Ustekinumab-hmny

Injection

130 mg/26 mL

(5 mg/mL)

For Intravenous Infusion Only

Must be diluted

Single-Dose Vial

Discard unused portion

130 mg/26 mL - Vial Carton Label

NDC 0143-9171-01

Rx only

Starjemza

Ustekinumab-hmny

Injection

130 mg/26 mL

(5 mg/mL)

For Intravenous Infusion Only

Must be diluted

Single-Dose Vial

Discard unused portion